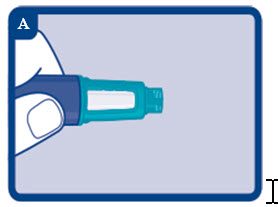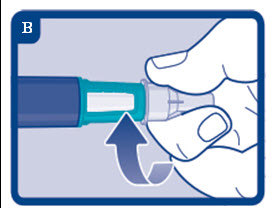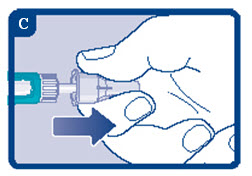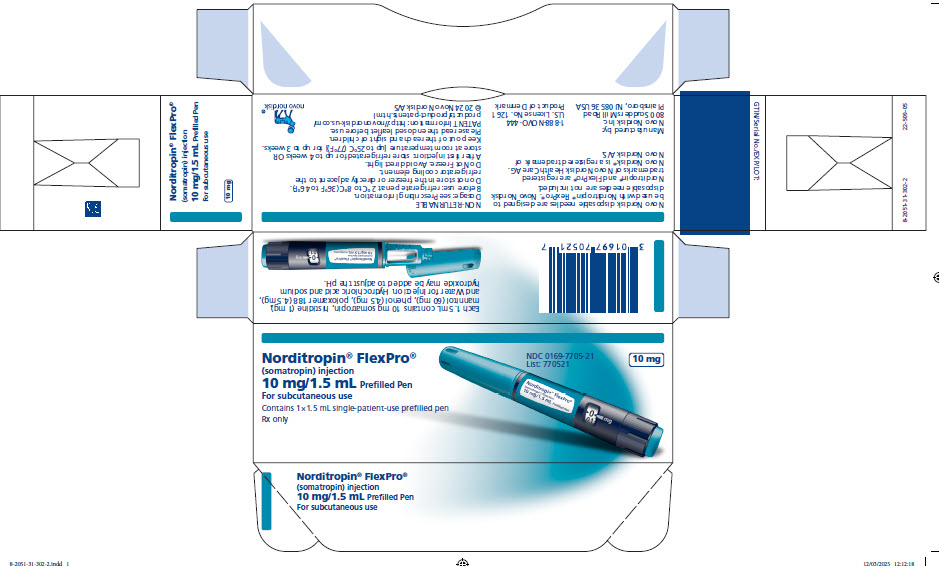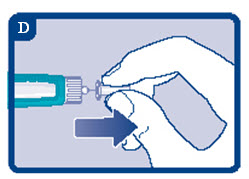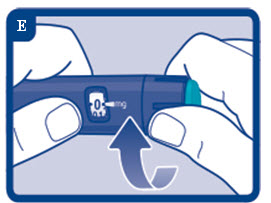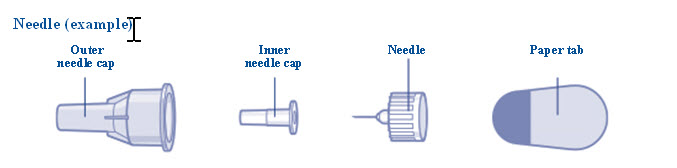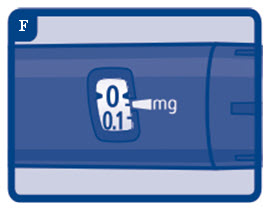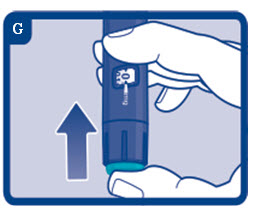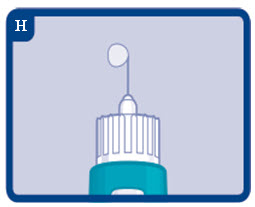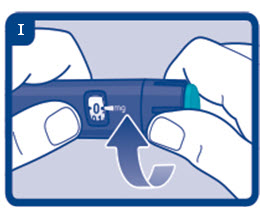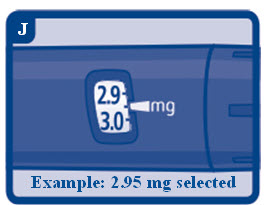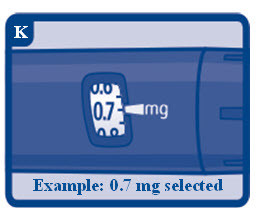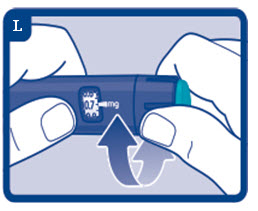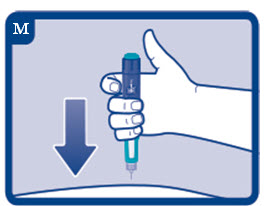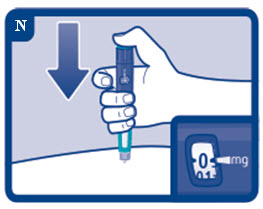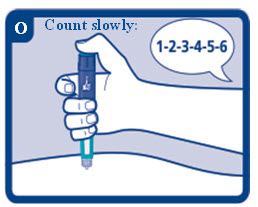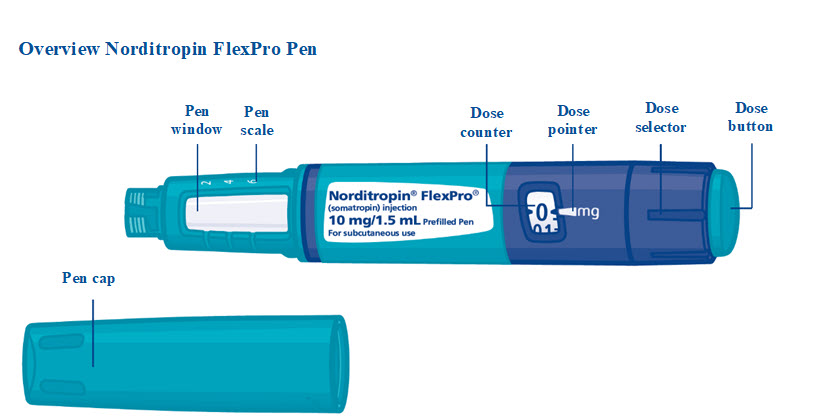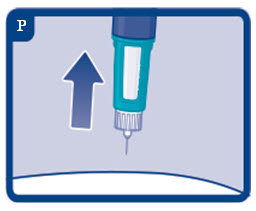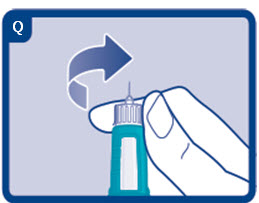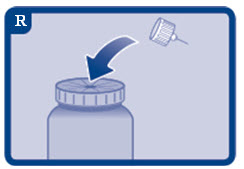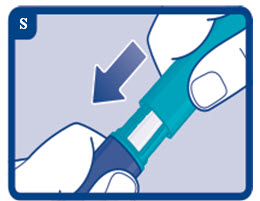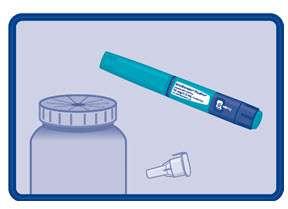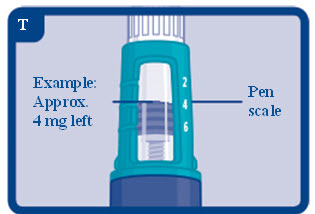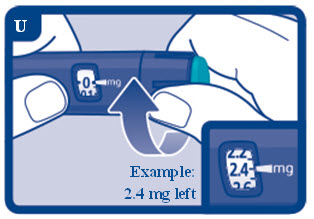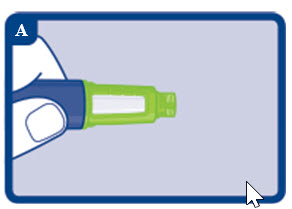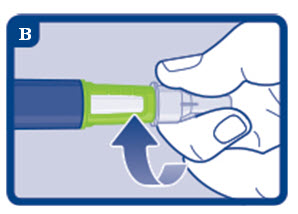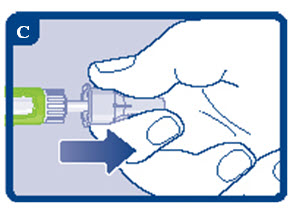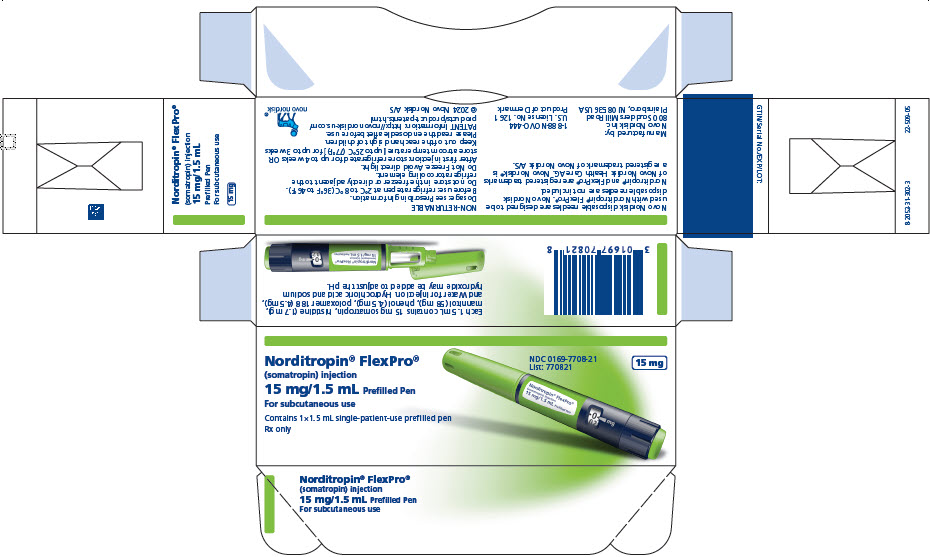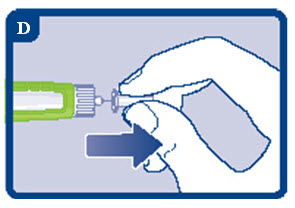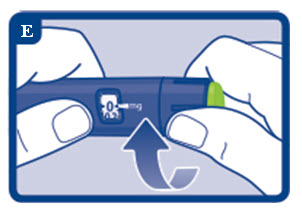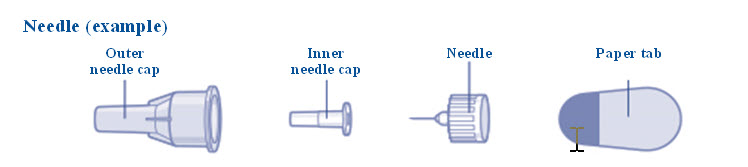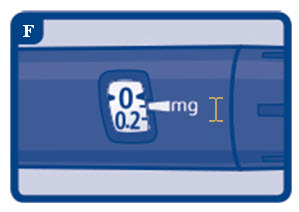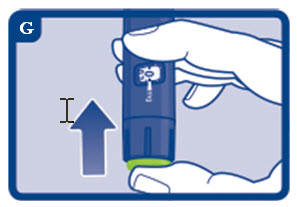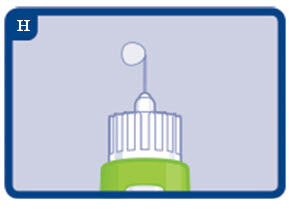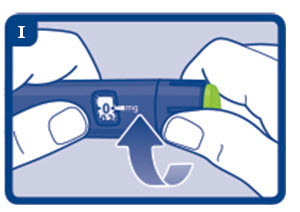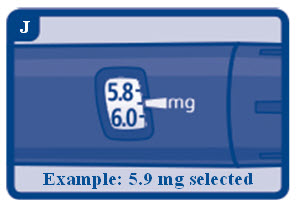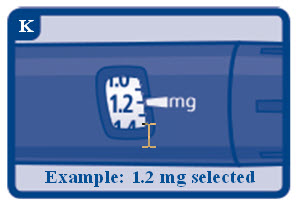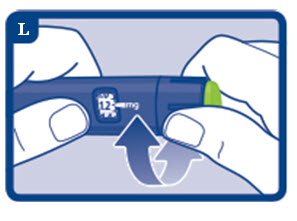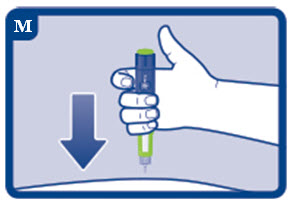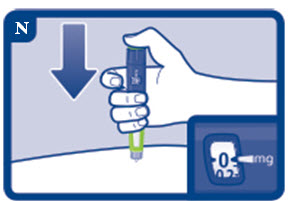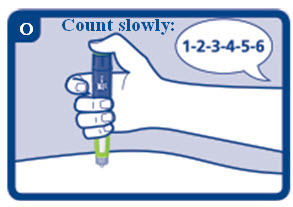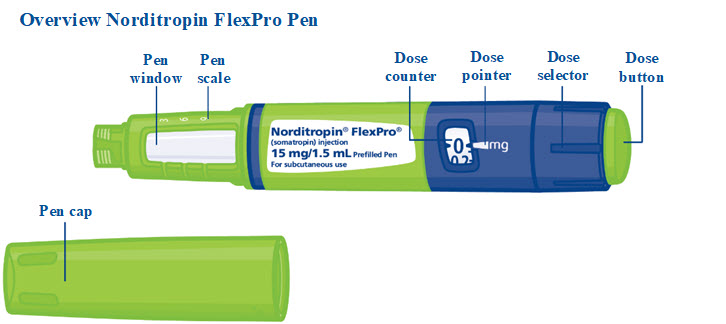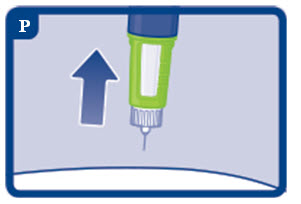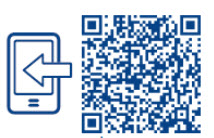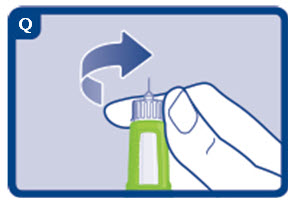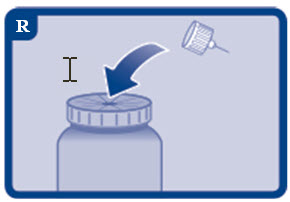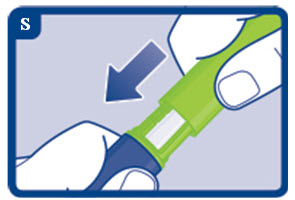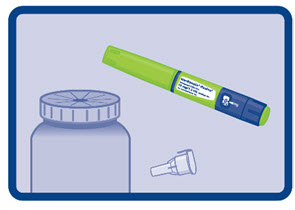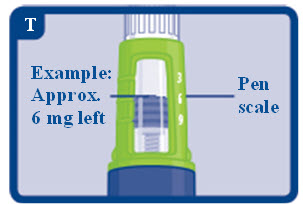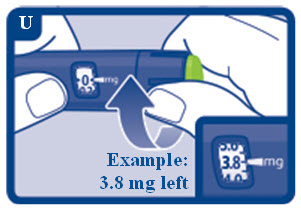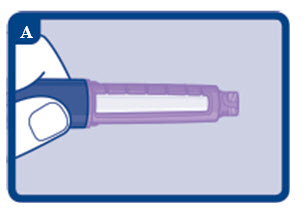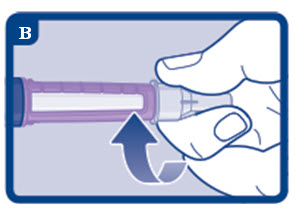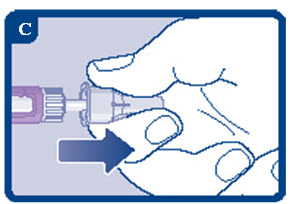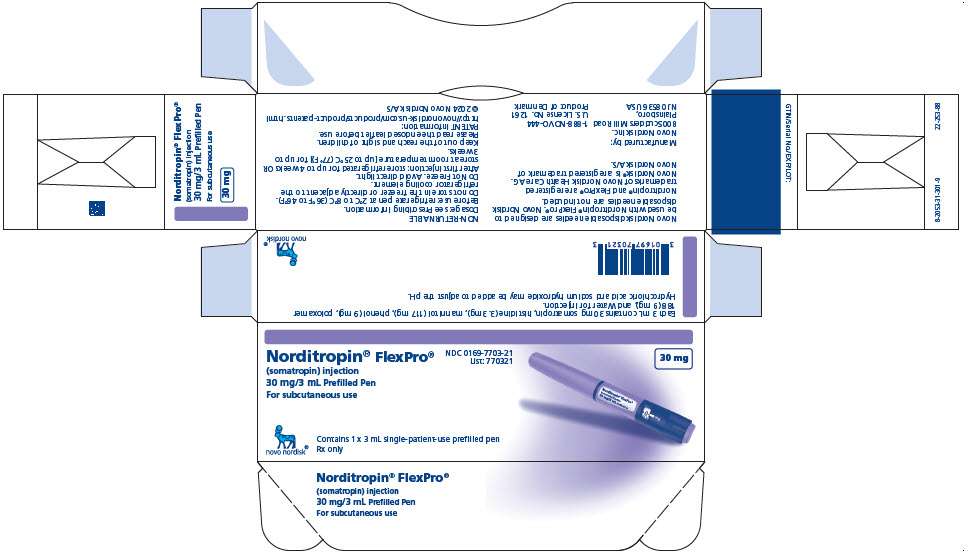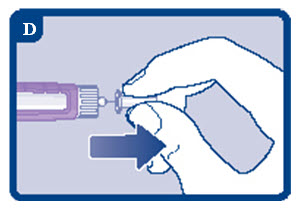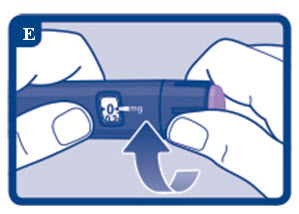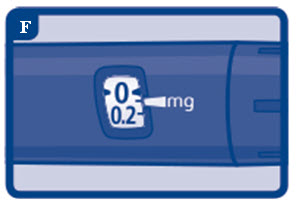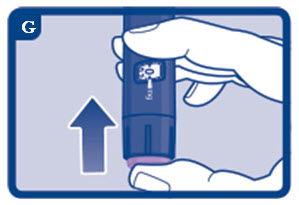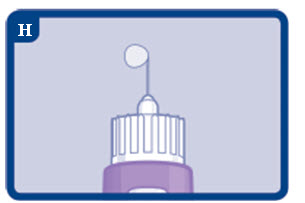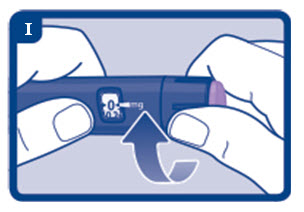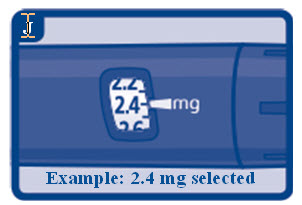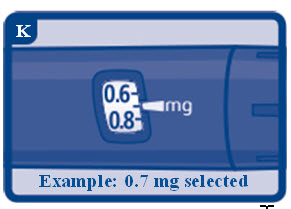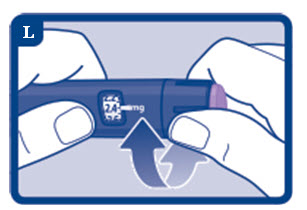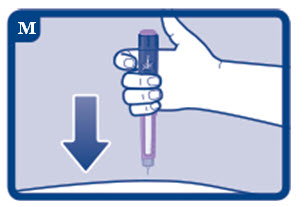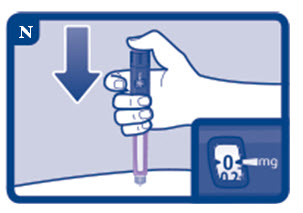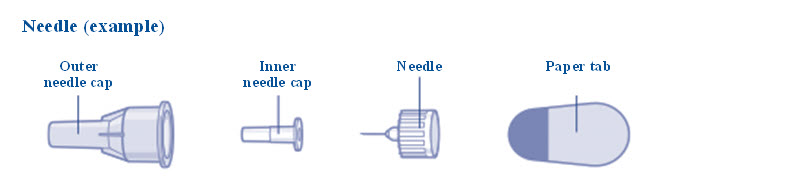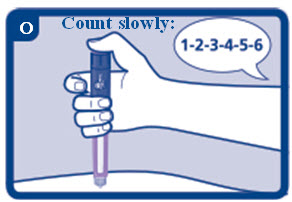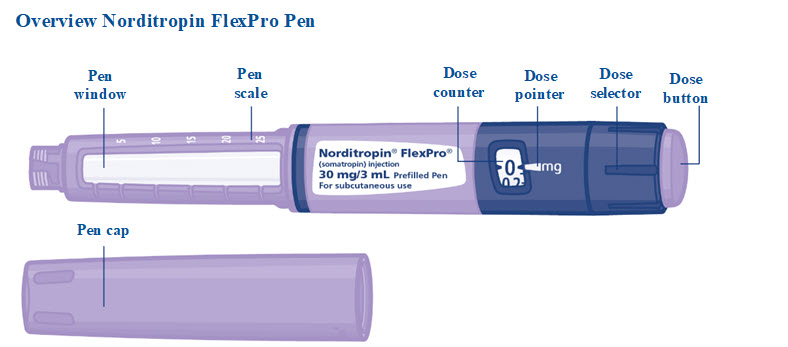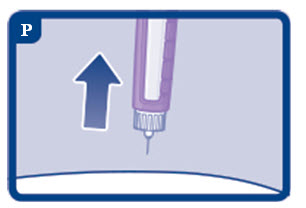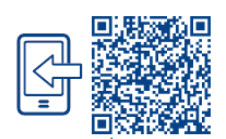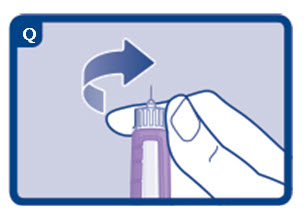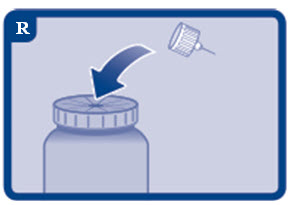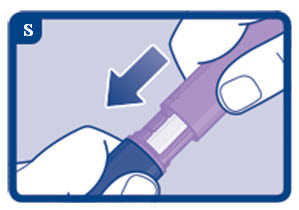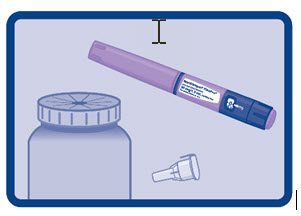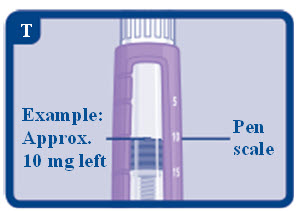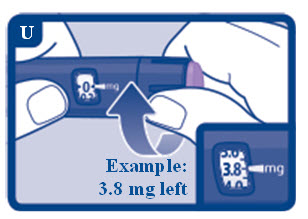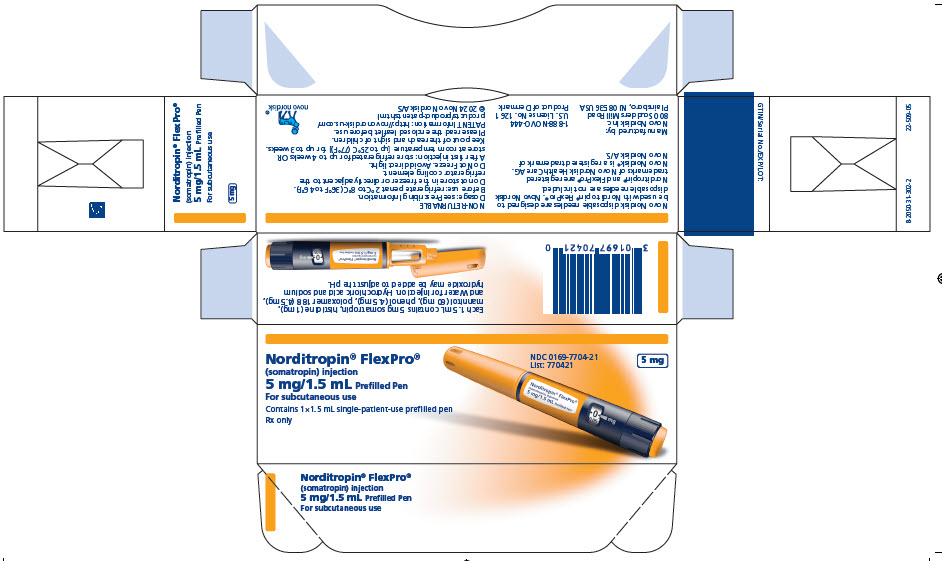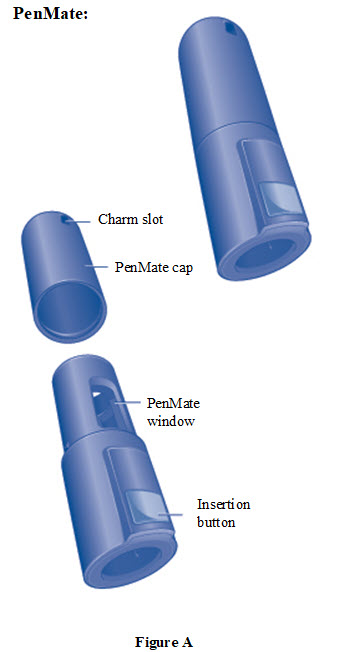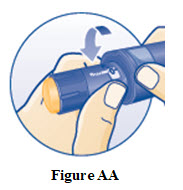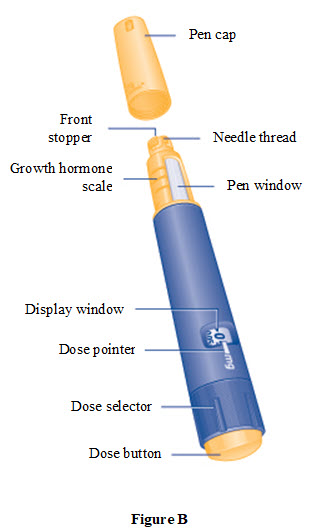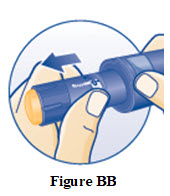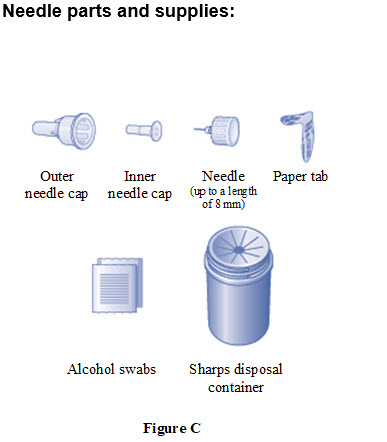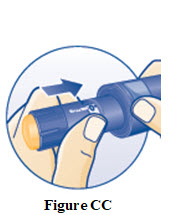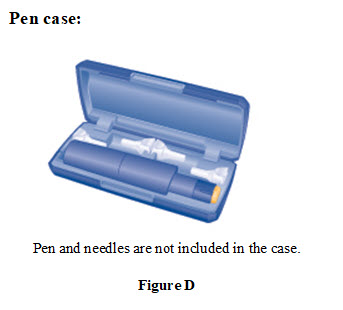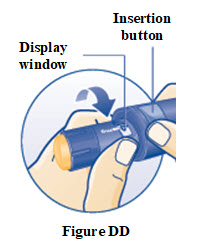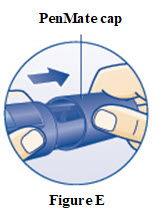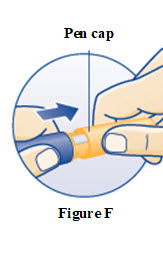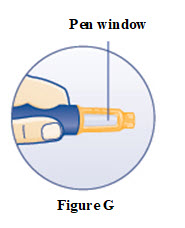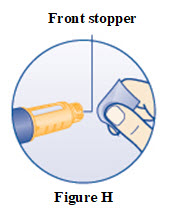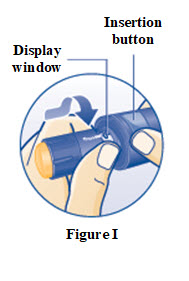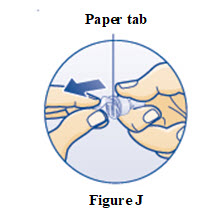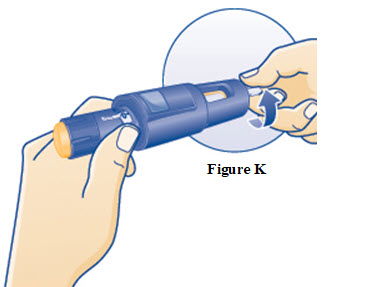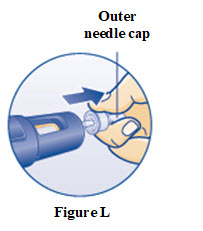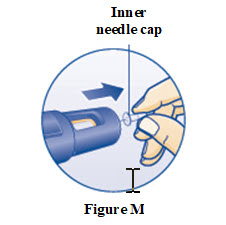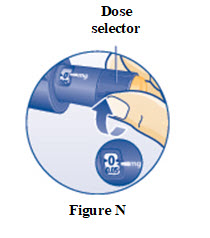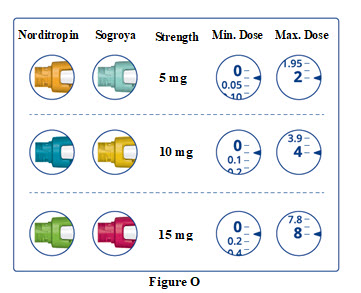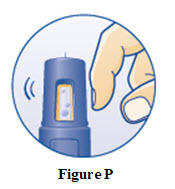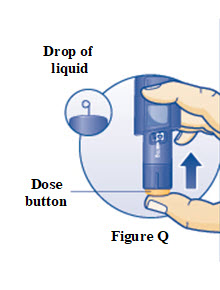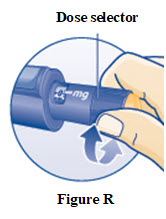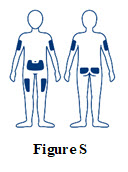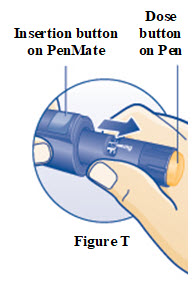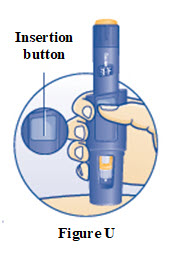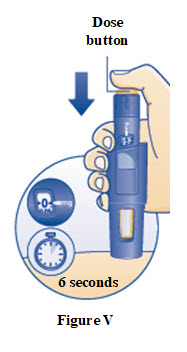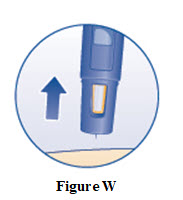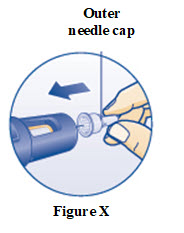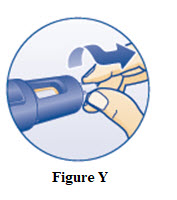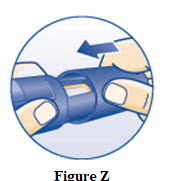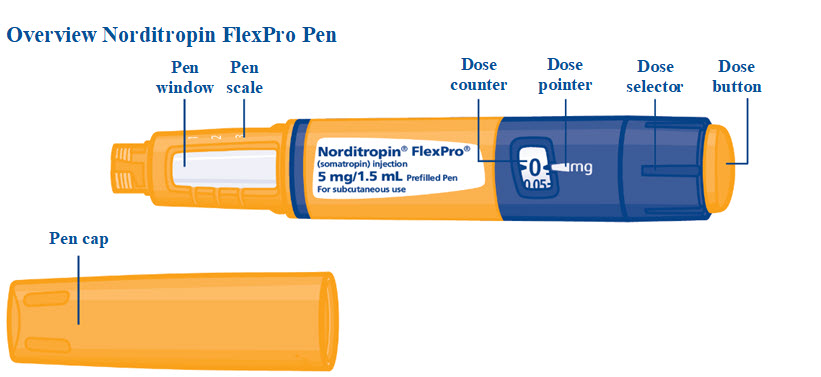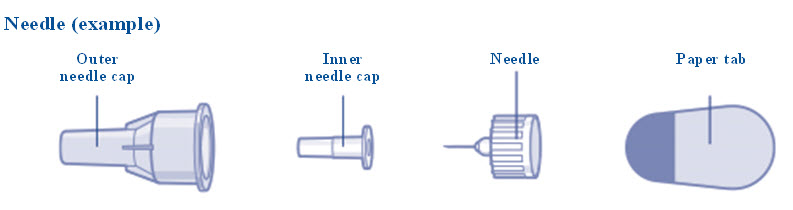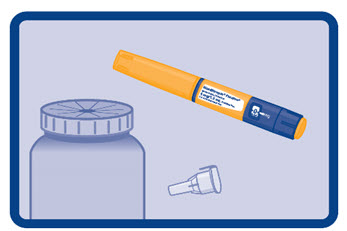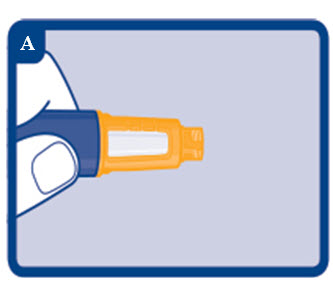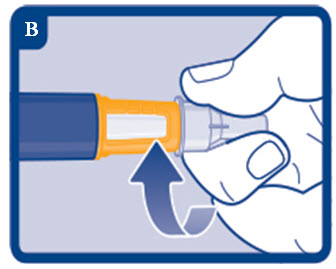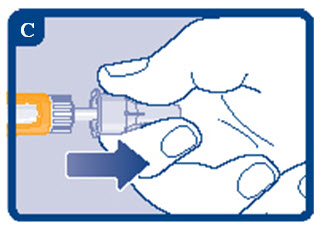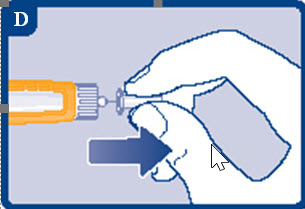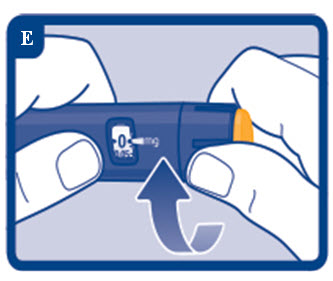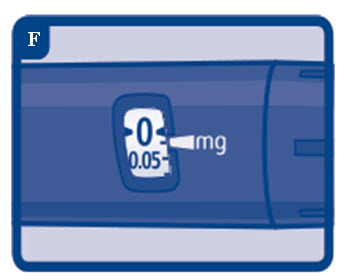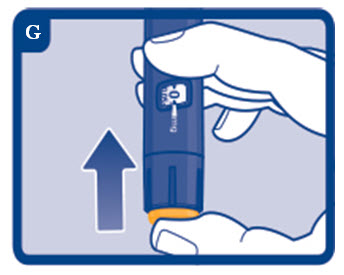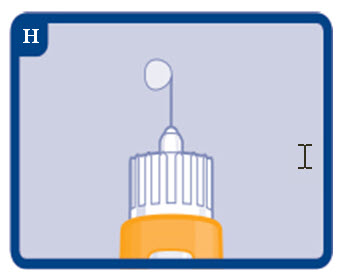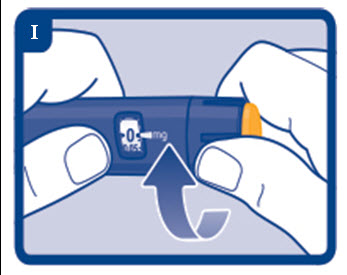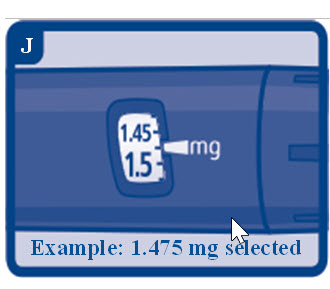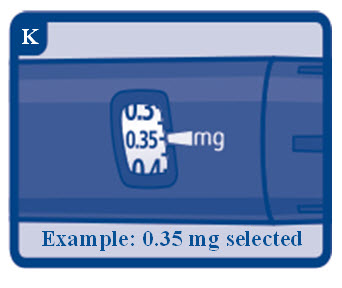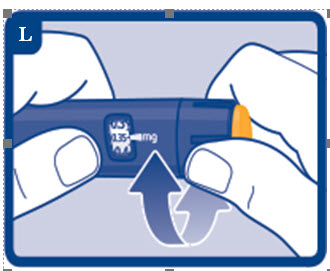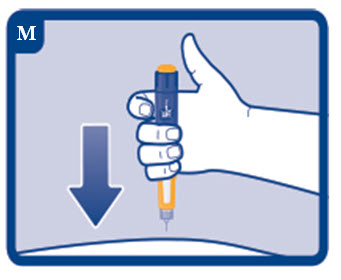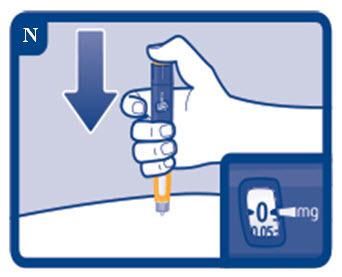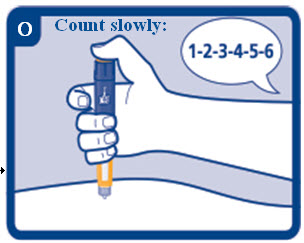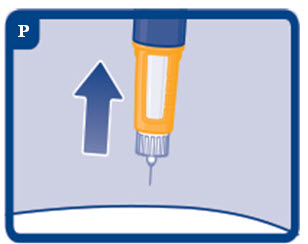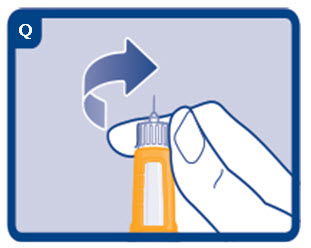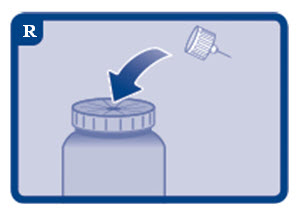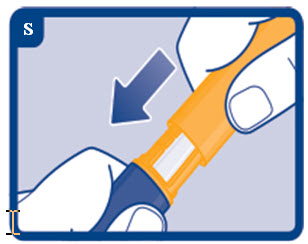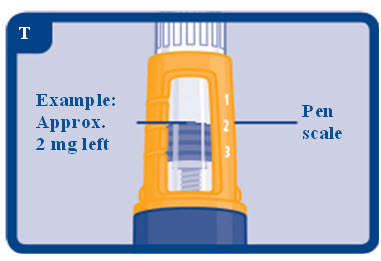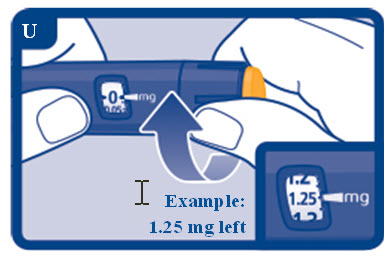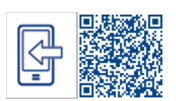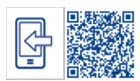 DRUG LABEL: Norditropin
NDC: 0169-7704 | Form: INJECTION, SOLUTION
Manufacturer: Novo Nordisk
Category: prescription | Type: HUMAN PRESCRIPTION DRUG LABEL
Date: 20250707

ACTIVE INGREDIENTS: SOMATROPIN 5 mg/1.5 mL
INACTIVE INGREDIENTS: HISTIDINE 1 mg/1.5 mL; HYDROCHLORIC ACID; MANNITOL 60 mg/1.5 mL; PHENOL 4.5 mg/1.5 mL; POLOXAMER 188 4.5 mg/1.5 mL; SODIUM HYDROXIDE; WATER

HIGHLIGHTS OF PRESCRIBING INFORMATION

These highlights do not include all the information needed to use NORDITROPIN® safely and effectively. See full prescribing information for NORDITROPIN.
NORDITROPIN (somatropin) injection, for subcutaneous use
Initial U.S. Approval: 1987

RECENT MAJOR CHANGES

Warnings and Precautions, Slipped Capital Femoral Epiphysis in Pediatric Patients (5.10)…..07/2025

1 INDICATIONS AND USAGE

NORDITROPIN is a recombinant human growth hormone indicated for:

- Pediatric: Treatment of pediatric patients with growth failure due to inadequate secretion of endogenous growth hormone (GH), short stature associated with Noonan syndrome, short stature associated with Turner syndrome, short stature born small for gestational age (SGA) with no catch-up growth by age 2 to 4 years, Idiopathic Short Stature (ISS), and growth failure due to Prader-Willi Syndrome (1.1)
- Adult: Replacement of endogenous GH in adults with growth hormone deficiency (1.2)

2 DOSAGE AND ADMINISTRATION

- Administer by subcutaneous injection to the back of upper arm, abdomen, buttock, or thigh with regular rotation of injection sites (2.1)
- Pediatric Dosage - divide the calculated weekly dosage into equal doses given either 6, or 7 days per week
  - GHD: 0.17 mg/kg/week to 0.24 mg/kg/week(2.2)
  - Noonan Syndrome: Up to 0.46 mg/kg/week (2.2)
  - Turner Syndrome: Up to 0.47 mg/kg/week (2.2)
  - SGA: Up to 0.47 mg/kg/week (2.2)
  - ISS: Up to 0.47 mg/kg/week (2.2)
  - Prader-Willi Syndrome: 0.24 mg/kg/week (2.2)
- Adult Dosage: Either of the following two dosing regimens may be used:
  - Non-weight based dosing: Initiate with a dose of approximately 0.2 mg/day (range, 0.15 mg/day-0.3 mg/day) and increase the dose every 1-2 months by increments of approximately 0.1 mg/day-0.2 mg/day, according to individual patient requirements (2.3)
  - Weight-based dosing (Not recommended for obese patients): Initiate at 0.004 mg/kg daily and increase the dose according to individual patient requirements to a maximum of 0.016 mg/kg daily (2.3)

3 DOSAGE FORMS AND STRENGTHS

Injection:

- 5 mg/1.5 mL: FlexPro single-patient-use pen (3)
- 10 mg/1.5 mL: FlexPro single-patient-use pen (3)
- 15 mg/1.5 mL: FlexPro single-patient-use pen (3)
- 30 mg/3 mL: FlexPro single-patient-use pen (3)

4 CONTRAINDICATIONS

- Acute Critical Illness (4)
- Pediatric patients with Prader-Willi syndrome who are severely obese, have history of severe upper airway obstruction, or have severe respiratory impairment due to risk of sudden death (4)
- Active Malignancy (4)
- Hypersensitivity to somatropin or excipients (4)
- Active Proliferative or Severe Non-Proliferative Diabetic Retinopathy (4)
- Pediatric patients with closed epiphyses (4)

5 WARNINGS AND PRECAUTIONS

- Increased Risk of Neoplasms: Second neoplasms have occurred in childhood cancer survivors. Monitor patients with preexisting tumors for progression or recurrence. (5.3)
- Glucose Intolerance and Diabetes Mellitus: NORDITROPIN may decrease insulin sensitivity, particularly at higher doses. Monitor glucose levels periodically in all patients receiving NORDITROPIN, especially in patients with existing diabetes mellitus or at risk for development. (5.4)
- Intracranial Hypertension (IH): Has been reported usually within 8 weeks of initiation. Perform fundoscopic examinations prior to initiation and periodically thereafter. If papilledema occurs, stop treatment. (5.5)
- Severe Hypersensitivity: Serious hypersensitivity reactions may occur. In the event of an allergic reaction, seek prompt medical attention. (5.6)
- Fluid Retention: May occur in adults and may be dose dependent. (5.7)
- Hypoadrenalism: Monitor patients for reduced serum cortisol levels and/or need for glucocorticoid dose increases in those with known hypoadrenalism. (5.8)
- Hypothyroidism: Monitor thyroid function periodically as hypothyroidism may occur or worsen after initiation of somatropin. (5.9)
- Slipped Capital Femoral Epiphysis in Pediatric Patients: May occur; evaluate patients with onset of a limp or hip/knee pain. (5.10)
- Progression of Preexisting Scoliosis in Pediatric Patients: Monitor patients with scoliosis for progression. (5.11)
- Pancreatitis: Has been reported; consider pancreatitis in patients with abdominal pain, especially pediatric patients. (5.12)

6 ADVERSE REACTIONS

Common adverse reactions in adult and pediatric patients include: upper respiratory infection, fever, pharyngitis, headache, otitis media, edema, arthralgia, paresthesia, myalgia, peripheral edema, flu syndrome, and impaired glucose tolerance. (6)

To report SUSPECTED ADVERSE REACTIONS, contact Novo Nordisk at 1-888-NOVO-444 (1-888-668-6444) or FDA at 1-800-FDA-1088 or www.fda.gov/medwatch.

7 DRUG INTERACTIONS

- Glucocorticoids: Patients treated with glucocorticoid for hypoadrenalism may require an increase in their maintenance or stress doses following initiation of NORDITROPIN (7)
- Pharmacologic Glucocorticoid Therapy and Supraphysiologic Glucocorticoid Treatment: Adjust glucocorticoid replacement dosing in pediatric patients receiving glucocorticoid treatment to avoid both hypoadrenalism and an inhibitory effect on growth. (7)
- Cytochrome P450-Metabolized Drugs: NORDITROPIN may alter the clearance. Monitor carefully if used with NORDITROPIN (7)
- Oral Estrogen: Larger doses of NORDITROPIN may be required (7)
- Insulin and/or Other Hypoglycemic Agents: Dose adjustment of insulin or hypoglycemic agent may be required (5.4, 7)

FULL PRESCRIBING INFORMATION

1 INDICATIONS AND USAGE

1.1 Pediatric Patients

NORDITROPIN is indicated for the treatment of pediatric patients with:

- growth failure due to inadequate secretion of endogenous growth hormone (GH),
- short stature associated with Noonan syndrome,
- short stature associated with Turner syndrome,
- short stature born small for gestational age (SGA) with no catch-up growth by age 2 years to 4 years of age,
- Idiopathic Short Stature (ISS), height standard deviation score (SDS) <-2.25, and associated with growth rates unlikely to permit attainment of adult height in the normal range,
- growth failure due to Prader-Willi syndrome (PWS).

1.2 Adult Patients

NORDITROPIN is indicated for the replacement of endogenous GH in adults with growth hormone deficiency (GHD)

2 DOSAGE AND ADMINISTRATION

2.1 Administration and Use Instructions

- Therapy with NORDITROPIN should be supervised by a physician who is experienced in the diagnosis and management of patients with the conditions for which NORDITROPIN is indicated [see Indications and Usage (1)].
- Fundoscopic examination should be performed routinely before initiating treatment with NORDITROPIN to exclude preexisting papilledema, and periodically thereafter [see Warnings and Precautions (5.5)].
- Administer NORDITROPIN by subcutaneous injection to the back of the upper arm, abdomen, buttocks, or thigh with regular rotation of injection sites to avoid lipoatrophy.
- Inspect visually for particulate matter and discoloration. NORDITROPIN should be clear and colorless. If the solution is cloudy or contains particulate matter do not use.
- Instructions for delivering the dosage are provided in the PATIENT INFORMATION and INSTRUCTIONS FOR USE leaflets enclosed with the NORDITROPIN FlexPro prefilled pen.

2.2 Pediatric Dosage

- Individualize dosage for each patient based on the growth response.
- Divide the calculated weekly NORDITROPIN dosage into equal doses given either 6, or 7 days per week.
- The recommended weekly dose in milligrams (mg) per kilogram (kg) of body weight for pediatric patients is:
- Pediatric GH Deficiency: 0.17 mg/kg/week to 0.24 mg/kg/week (0.024 to 0.034 mg/kg/day)
- Noonan Syndrome: Up to 0.46 mg/kg/week (up to 0.066 mg/kg/day)
- Turner Syndrome: Up to 0.47 mg/kg/week (up to 0.067 mg/kg/day)
- Small for Gestational Age (SGA): Up to 0.47 mg/kg/week (up to 0.067 mg/kg/day)
  - In very short pediatric patients, HSDS less than -3, and older pubertal pediatric patients consider initiating treatment with a larger dose of NORDITROPIN (up to 0.067 mg/kg/day). Consider a gradual reduction in dosage if substantial catch-up growth is observed during the first few years of therapy. In pediatric patients less than 4 years of age with less severe short stature, baseline HSDS values between -2 and -3, consider initiating treatment at 0.033 mg/kg/day and titrate the dose as needed.
- Idiopathic Short Stature: Up to 0.47 mg/kg/week (up to 0.067 mg/kg/day)
- Prader-Willi Syndrome: 0.24 mg/kg/week (0.034 mg/kg/day)
- Assess compliance and evaluate other causes of poor growth such as hypothyroidism, under-nutrition, advanced bone age and antibodies to recombinant human growth hormone if patients experience failure to increase height velocity, particularly during the first year of treatment.
- Discontinue NORDITROPIN for stimulation of linear growth once epiphyseal fusion has occurred [see Contraindications (4)].

2.3 Adult Dosage

- Patients who were treated with somatropin for GH deficiency in childhood and whose epiphyses are closed should be reevaluated before continuation of somatropin for GH deficient adults.
- Consider using a lower starting dose and smaller dose increment increases for geriatric patients as they may be at increased risk for adverse reactions with NORDITROPIN than younger individuals [see Use in Specific Populations (8.5)].
- Estrogen-replete women and patients receiving oral estrogen may require higher doses [see Drug Interactions (7)].
- Administer the prescribed dose daily.
- Either of two NORDITROPIN dosing regimens may be used:
- Non-weight based
- Initiate NORDITROPIN with a dose of approximately 0.2 mg/day (range, 0.15 mg/day to 0.3 mg/day) and increase the dose every 1-2 months by increments of approximately 0.1 mg/day to 0.2 mg/day, according to individual patient requirements based on the clinical response and serum insulin-like growth factor 1 (IGF-1) concentrations.
- Decrease the dose as necessary on the basis of adverse reactions and/or serum IGF-1 concentrations above the age- and gender-specific normal range.
- Maintenance dosages will vary considerably from person to person, and between male and female patients.
- Weight-based
- Initiate NORDITROPIN at 0.004 mg/kg daily and increase the dose according to individual patient requirements to a maximum of 0.016 mg/kg daily.
- Use the patient’s clinical response, adverse reactions, and determination of age- and gender-adjusted serum IGF-1 concentrations as guidance in dose titration.
- Not recommended for obese patients as they are more likely to experience adverse reactions with this regimen

3 DOSAGE FORMS AND STRENGTHS

Injection: NORDITROPIN is available as a clear and colorless solution in a

- 5 mg/1.5 mL FlexPro single-patient-use pen (orange)
- 10 mg/1.5 mL FlexPro single-patient-use pen (blue)
- 15 mg/1.5 mL FlexPro single-patient-use pen (green)
- 30 mg/3 mL FlexPro single-patient-use pen (purple)

4 CONTRAINDICATIONS

NORDITROPIN is contraindicated in patients with:

- Acute critical illness after open heart surgery, abdominal surgery or multiple accidental trauma, or those with acute respiratory failure due to the risk of increased mortality with use of pharmacologic doses of somatropin [see Warnings and Precautions (5.1)].
- Pediatric patients with Prader-Willi syndrome who are severely obese, have a history of upper airway obstruction or sleep apnea, or have severe respiratory impairment due to the risk of sudden death [see Warnings and Precautions (5.2)].
- Active Malignancy [see Warnings and Precautions (5.3)].
- Hypersensitivity to NORDITROPIN or any of its excipients. Systemic hypersensitivity reactions have been reported with postmarketing use of somatropins [see Warnings and Precautions (5.6)].
- Active proliferative or severe non-proliferative diabetic retinopathy.
- Pediatric patients with closed epiphyses.

5 WARNINGS AND PRECAUTIONS

5.1 Increased Mortality in Patients with Acute Critical Illness

Increased mortality in patients with acute critical illness due to complications following open heart surgery, abdominal surgery or multiple accidental trauma, or those with acute respiratory failure has been reported after treatment with pharmacologic amounts of somatropin [see Contraindications (4)]. Two placebo-controlled clinical trials in non-growth hormone deficient adult patients (n=522) with these conditions in intensive care units revealed a significant increase in mortality (42% vs. 19%) among somatropin-treated patients (doses 5.3-8 mg/day) compared to those receiving placebo. The safety of continuing NORDITROPIN treatment in patients receiving replacement doses for approved indications who concurrently develop these illnesses has not been established. NORDITROPIN is not indicated for the treatment of non-GH deficient adults.

5.2 Sudden Death in Pediatric Patients with Prader-Willi Syndrome

There have been reports of sudden death after initiating therapy with somatropin in pediatric patients with Prader-Willi syndrome who had one or more of the following risk factors: severe obesity, history of upper airway obstruction or sleep apnea, or unidentified respiratory infection. Male patients with one or more of these factors may be at greater risk than females. Patients with Prader-Willi syndrome should be evaluated for signs of upper airway obstruction and sleep apnea before initiation of treatment with somatropin. If, during treatment with NORDITROPIN, patients show signs of upper airway obstruction (including onset of or increased snoring) and/or new onset sleep apnea, treatment should be interrupted. All patients with Prader-Willi syndrome treated with NORDITROPIN should also have effective weight control and be monitored for signs of respiratory infection, which should be diagnosed as early as possible and treated aggressively [see Contraindications (4)].

5.3 Increased Risk of Neoplasms

Active Malignancy

There is an increased risk of malignancy progression with somatropin treatment in patients with active malignancy [See Contraindications (4)]. Any preexisting malignancy should be inactive and its treatment complete prior to instituting therapy with NORDITROPIN. Discontinue NORDITROPIN if there is evidence of recurrent activity.

Risk of Second Neoplasm in Pediatric Patients

There is an increased risk of a second neoplasm in pediatric cancer survivors who were treated with radiation to the brain/head and who developed subsequent GH deficiency and were treated with somatropin. Intracranial tumors, in particular meningiomas, were the most common of these second neoplasms. In adults, it is unknown whether there is any relationship between somatropin replacement therapy and CNS tumor recurrence. Monitor all patients receiving NORDITROPIN who have a history of GH deficiency secondary to an intracranial neoplasm for progression or recurrence of the tumor.

New Malignancy During Treatment

Because pediatric patients with certain rare genetic causes of short stature have an increased risk of developing malignancies, thoroughly consider the risks and benefits of starting NORDITROPIN in these patients. If NORDITROPIN is initiated, carefully monitor patients for development of neoplasms.

Monitor all patients receiving NORDITROPIN carefully for increased growth, or potential malignant changes, of preexisting nevi. Advise patients/caregivers to report marked changes in behavior, onset of headaches, vision disturbances and/or changes in skin pigmentation or changes in the appearance of pre-existing nevi.

5.4 Glucose Intolerance and Diabetes Mellitus

Treatment with somatropin may decrease insulin sensitivity, particularly at higher doses. New onset type 2 diabetes mellitus has been reported in patients taking somatropin. Previously undiagnosed impaired glucose tolerance and overt diabetes mellitus may be unmasked. Monitor glucose levels periodically in all patients receiving NORDITROPIN, especially in those with risk factors for diabetes mellitus, such as obesity, Turner syndrome, or a family history of diabetes mellitus. Patients with preexisting type 1 or type 2 diabetes mellitus or impaired glucose tolerance should be monitored closely. The doses of antidiabetic agents may require adjustment when NORDITROPIN is initiated.

5.5 Intracranial Hypertension

Intracranial hypertension (IH) with papilledema, visual changes, headache, nausea, and/or vomiting has been reported in a small number of patients treated with somatropins. Symptoms usually occurred within the first eight (8) weeks after the initiation of somatropin therapy. In all reported cases, IH-associated signs and symptoms rapidly resolved after cessation of therapy or a reduction of the somatropin dose. Funduscopic examination should be performed routinely before initiating treatment with NORDITROPIN to exclude preexisting papilledema, and periodically thereafter. If papilledema is observed by funduscopy during somatropin treatment, treatment should be stopped. If somatropin-induced IH is diagnosed, treatment with NORDITROPIN can be restarted at a lower dose after IH-associated signs and symptoms have resolved. Patients with Turner syndrome may be at increased risk for the development of IH.

5.6 Severe Hypersensitivity

Serious systemic hypersensitivity reactions including anaphylactic reactions and angioedema have been reported with postmarketing use of somatropins. Patients and caregivers should be informed that such reactions are possible and that prompt medical attention should be sought if an allergic reaction occurs [see Contraindications (4)].

5.7 Fluid Retention

Fluid retention during somatropin replacement therapy in adults may frequently occur. Clinical manifestations of fluid retention (e.g. edema, arthralgia, myalgia, nerve compression syndromes including carpal tunnel syndrome/paraesthesias) are usually transient and dose dependent.

5.8 Hypoadrenalism

Patients receiving somatropin therapy who have or are at risk for pituitary hormone deficiency(s) may be at risk for reduced serum cortisol levels and/or unmasking of central (secondary) hypoadrenalism. In addition, patients treated with glucocorticoid replacement for previously diagnosed hypoadrenalism may require an increase in their maintenance or stress doses following initiation of NORDITROPIN treatment. Monitor patients for reduced serum cortisol levels and/or need for glucocorticoid dose increases in those with known hypoadrenalism [see Drug Interactions (7)].

5.9 Hypothyroidism

Undiagnosed/untreated hypothyroidism may prevent an optimal response to NORDITROPIN, in particular, the growth response in pediatric patients. Patients with Turner syndrome have an inherently increased risk of developing autoimmune thyroid disease and primary hypothyroidism. In patients with GH deficiency, central (secondary) hypothyroidism may first become evident or worsen during somatropin treatment. Therefore, patients should have periodic thyroid function tests and thyroid hormone replacement therapy should be initiated or appropriately adjusted when indicated.

5.10 Slipped Capital Femoral Epiphysis in Pediatric Patients

Slipped capital femoral epiphysis may occur more frequently in patients with endocrine disorders (including GH deficiency and Turner syndrome) or in patients undergoing rapid growth. Slipped capital femoral epiphysis may lead to osteonecrosis. Cases of slipped capital femoral epiphysis with or without osteonecrosis have been reported in pediatric patients with short stature receiving somatropin, including NORDITROPIN. Evaluate pediatric patients receiving NORDITROPIN with the onset of a limp or complaints of hip or knee pain for slipped capital femoral epiphysis and osteonecrosis and manage accordingly.

5.11 Progression of Preexisting Scoliosis in Pediatric Patients

Somatropin increases the growth rate, and progression of existing scoliosis can occur in patients who experience rapid growth. Somatropin has not been shown to increase the occurrence of scoliosis. Monitor patients with a history of scoliosis for progression of scoliosis.

5.12 Pancreatitis

Cases of pancreatitis have been reported in pediatric patients and adults receiving somatropin products. There may be a greater risk in pediatric patients compared with adults. Published literature indicates that females who have Turner syndrome may be at greater risk than other pediatric patients receiving somatropin products. Pancreatitis should be considered in patients who develop persistent severe abdominal pain.

5.13 Lipoatrophy

When somatropin products are administered subcutaneously at the same site over a long period of time, tissue atrophy may result. Rotate injection sites when administering NORDITROPIN to reduce this risk [see Administration and Use Instructions (2.1)].

5.14 Laboratory Tests

Serum levels of inorganic phosphorus, alkaline phosphatase, parathyroid hormone (PTH) and IGF-I may increase after NORDITROPIN treatment.

6 ADVERSE REACTIONS

The following important adverse reactions are also described elsewhere in the labeling:

- Increased mortality in patients with acute critical illness [see Warnings and Precautions (5.1)]
- Sudden death in children with Prader-Willi syndrome [see Warnings and Precautions (5.2)]
- Neoplasms [see Warnings and Precautions (5.3)]
- Glucose intolerance and diabetes mellitus [see Warnings and Precautions (5.4)]
- Intracranial hypertension [see Warnings and Precautions (5.5)]
- Severe hypersensitivity [see Warnings and Precautions (5.6)]
- Fluid retention [see Warnings and Precautions (5.7)]
- Hypoadrenalism [see Warnings and Precautions (5.8)]
- Hypothyroidism [see Warnings and Precautions (5.9)]
- Slipped capital femoral epiphysis in pediatric patients [see Warnings and Precautions (5.10)]
- Progression of preexisting scoliosis in pediatric patients [see Warnings and Precautions (5.11)]
- Pancreatitis [see Warnings and Precautions (5.12)]
- Lipoatrophy [see Warnings and Precautions (5.13)]

6.1 Clinical Trials Experience

Because clinical trials are conducted under varying conditions, adverse reaction rates observed during the clinical trials performed with one somatropin product cannot always be directly compared to the rates observed during the clinical trials performed with another somatropin product, and may not reflect the adverse reaction rates observed in practice.

Pediatric Patients

Growth Failure due to Inadequate Secretion of Endogenous Growth Hormone

In one randomized, open label, clinical study the most frequent adverse reactions were headache, pharyngitis, otitis media and fever. There were no clinically significant differences between the three doses assessed in the study (0.025, 0.05 and 0.1 mg/kg/day).

Short Stature Associated with Noonan Syndrome

NORDITROPIN was studied in 21 pediatric patients, 3 years to 14 years of age at doses of 0.033 mg/kg/day and 0.066 mg/kg/day. After the two-year study, patients continued NORDITROPIN treatment until final height was achieved; randomized dose groups were not maintained. Adverse reactions were later collected retrospectively from 18 pediatric patients; total follow-up was 11 years. An additional 6 pediatric patients were not randomized, but followed the protocol and are included in this assessment of adverse reactions.

The most frequent adverse reactions were upper respiratory infection, gastroenteritis, ear infection, and influenza. Cardiac disorders was the system organ class with the second most adverse reactions reported. Scoliosis was reported in 1 and 4 pediatric patients receiving doses of 0.033 mg/kg/day and 0.066 mg/kg/day respectively. The following additional adverse reactions also occurred once: insulin resistance and panic reaction for the 0.033 mg/kg/day dose group; injection site pruritus, bone development abnormal, depression, and self-injurious ideation in the 0.066 mg/kg/day dose group. Headache occurred in 2 cases in the 0.066 mg/kg/day dose group.

Short Stature Associated with Turner Syndrome

In two clinical studies in pediatric patients that were treated until final height with various doses of NORDITROPIN, the most frequently reported adverse reactions were influenza-like illness, otitis media, upper respiratory tract infection, otitis externa, gastroenteritis, eczema and, impaired fasting glucose. Adverse reactions in study 1 were most frequent in the highest dose groups. Three patients in study 1 had excessive growth of hands and/or feet in the high dose groups. Two patients in study 1 had a serious adverse reaction of exacerbation of preexisting scoliosis in the 0.045 mg/kg/day group.

Small for Gestational Age (SGA) with No Catch-up Growth by Age 2-4 Years

In a study, 53 pediatric patients were treated with 2 doses of NORDITROPIN (0.033 or 0.067 mg/kg/day) to final height for up to 13 years (mean duration of treatment 7.9 and 9.5 years for girls and boys, respectively). The most frequently reported adverse reactions were influenza-like illness, upper respiratory tract infection, bronchitis, gastroenteritis, abdominal pain, otitis media, pharyngitis, arthralgia, headache, gynecomastia, and increased sweating. One pediatric patient treated with 0.067 mg/kg/day for 4 years was reported with disproportionate growth of the lower jaw, and another patient treated with 0.067 mg/kg/day developed a melanocytic nevus. 4 pediatric patients treated with 0.067 mg/kg/day and 2 pediatric patients treated with 0.033 mg/kg/day of NORDITROPIN had increased fasting blood glucose levels after 1 year of treatment. In addition, small increases in mean fasting blood glucose and insulin levels after 1 and 2 years of NORDITROPIN treatment appeared to be dose-dependent.

In a second study, 98 Japanese pediatric patients were treated with 2 doses of NORDITROPIN (0.033 or 0.067 mg/kg/day) for 2 years or were untreated for 1 year. Adverse reactions were otitis media, arthralgia and impaired glucose tolerance. Arthralgia and transiently impaired glucose tolerance were reported in the 0.067 mg/kg/day treatment group.

Idiopathic Short Stature

In two open-label clinical studies with another somatropin product in pediatric patients, the most common adverse reactions were upper respiratory tract infections, influenza, tonsillitis, nasopharyngitis, gastroenteritis, headaches, increased appetite, pyrexia, fracture, altered mood, and arthralgia.

Growth Failure Due to Prader-Willi Syndrome

In two clinical studies in pediatric patients with PWS carried out with another somatropin product, the following adverse reactions were reported: edema, aggressiveness, arthralgia, benign intracranial hypertension, hair loss, headache, and myalgia.

Adult Patients

Adults with Growth Hormone Deficiency

Adverse reactions with an incidence of ≥5% occurring in patients with AO GHD during the 6 month placebo-controlled portion of a clinical trial for NORDITROPIN are presented in Table 1.

Table 1 – Adverse Reactions with ≥5% Overall Incidence in Adult Onset Growth Hormone

Deficient Patients Treated with NORDITROPIN During a Six Month Placebo-Controlled Clinical Trial

 | Placebo; (N=52) | NORDITROPIN; (N=53)
Adverse Reactions | % | %
Peripheral Edema | 8 | 42
Edema | 0 | 25
Arthralgia | 15 | 19
Leg Edema | 4 | 15
Myalgia | 8 | 15
Infection (non-viral) | 8 | 13
Paraesthesia | 6 | 11
Skeletal Pain | 2 | 11
Headache | 6 | 9
Bronchitis | 0 | 9
Flu-like symptoms | 4 | 8
Hypertension | 2 | 8
Gastroenteritis | 8 | 8
Other Non-Classifiable Disorders (excludes accidental injury) | 6 | 8
Increased sweating | 2 | 8
Glucose tolerance abnormal | 2 | 6
Laryngitis | 6 | 6
Type 2 diabetes mellitus | 0 | 5

6.2 Postmarketing Experience

The following adverse reactions have been identified during post-approval use of somatropin or NORDITROPIN. Because these adverse reactions are reported voluntarily from a population of uncertain size, it is not always possible to reliably estimate their frequency or establish a causal relationship to drug exposure.

Immune system disorders — Serious systemic hypersensitivity reactions including anaphylactic reactions and angioedema

Skin — Increase in size or number of cutaneous nevi

Endocrine disorders — Hypothyroidism - Gynecomastia

Metabolism and nutrition disorders — Hyperglycemia

Musculoskeletal and connective tissue disorders — Slipped capital femoral epiphysis and osteonecrosis (including Legg-Calvé-Perthes disease) have been reported in pediatric patients treated with growth hormone [see Warnings and Precautions (5.10)]. Cases have been reported with NORDITROPIN.

Investigations — Increase in blood alkaline phosphatase level — Decrease in serum thyroxin (T4) levels

Gastrointestinal — Pancreatitis

Neoplasm — Leukemia has been reported in a small number of GH deficient children treated with somatropin, somatrem (methionylated rhGH) and GH of pituitary origin

7 DRUG INTERACTIONS

Table 2 includes a list of drugs with clinically important drug interactions when administered concomitantly with NORDITROPIN and instructions for preventing or managing them.

Table 2: Clinically Important Drug Interactions with NORDITROPIN

Glucocorticoids
Clinical Impact: | Microsomal enzyme 11β-hydroxysteroid dehydrogenase type 1 (11βHSD-1) is required for conversion of cortisone to its active metabolite, cortisol, in hepatic and adipose tissue. NORDITROPIN inhibits 11βHSD-1. Consequently, individuals with untreated GH deficiency have relative increases in 11βHSD-1 and serum cortisol. Initiation of NORDITROPIN may result in inhibition of 11βHSD-1 and reduced serum cortisol concentrations.
Intervention: | Patients treated with glucocorticoid replacement for hypoadrenalism may require an increase in their maintenance or stress doses following initiation of NORDITROPIN [see Warnings and Precautions (5.8)].
Examples: | Cortisone acetate and prednisone may be effected more than others since conversion of these drugs to their biologically active metabolites is dependent on the activity of 11βHSD-1.
Pharmacologic Glucocorticoid Therapy and Supraphysiologic Glucocorticoid Treatment
Clinical Impact: | Pharmacologic glucocorticoid therapy and supraphysiologic glucocorticoid treatment may attenuate the growth promoting effects of NORDITROPIN in pediatric patients.
Intervention: | Carefully adjust glucocorticoid replacement dosing in pediatric patients receiving glucocorticoid treatments to avoid both hypoadrenalism and an inhibitory effect on growth.
Cytochrome P450-Metabolized Drugs
Clinical Impact: | Limited published data indicate that somatropin treatment increases cytochrome P450 (CP450)-mediated antipyrine clearance. NORDITROPIN may alter the clearance of compounds known to be metabolized by CP450 liver enzymes.
Intervention: | Careful monitoring is advisable when NORDITROPIN is administered in combination with drugs metabolized by CP450 liver enzymes.
Oral Estrogen
Clinical Impact: | Oral estrogens may reduce the serum IGF-1 response to NORDITROPIN.
Intervention: | Patients receiving oral estrogen replacement may require greater NORDITROPIN dosages [see Dosage and Administration (2.3)].
Insulin and/or Other Hypoglycemic Agents
Clinical Impact: | Treatment with NORDITROPIN may decrease insulin sensitivity, particularly at higher doses.
Intervention: | Patients with diabetes mellitus may require adjustment of their doses of insulin and/or other hypoglycemic agents [see Warnings and Precautions (5.4)].

8 USE IN SPECIFIC POPULATIONS

8.1 Pregnancy

Risk Summary

Limited available data with somatropin use in pregnant women are insufficient to determine a drug-associated risk of adverse developmental outcomes. In animal reproduction studies, there was no evidence of fetal or neonatal harm when pregnant rats were administered subcutaneous NORDITROPIN during organogenesis or during lactation at doses approximately 10-times higher than the maximal clinical dose of 0.016 mg/kg, based on body surface area (see Data).

The estimated background risk of birth defects and miscarriage for the indicated population is unknown. In the U.S. general population, the estimated background risk of major birth defects and miscarriage in clinically recognized pregnancies is 2-4% and 15-20%, respectively.

Data

Animal Data

In an embryo-fetal development study, NORDITROPIN was administered via subcutaneous injection to pregnant rats from gestation Day 6 to 17, corresponding with the period of organogenesis. NORDITROPIN did not adversely affect fetal viability or developmental outcomes at maternal doses that were approximately 10-times the clinical dose of 0.016 mg/kg, based on body surface area.

In a pre- and post-natal development study in pregnant rats, NORDITROPIN was administered from gestation Day 17 through lactation Day 21 (weaning). No adverse developmental effects were observed in the offspring at doses up to 1.1 mg/kg (approximately 10 times the clinical dose of 0.016 mg/kg, based on body surface area).

8.2 Lactation

Risk Summary

There is no information regarding the presence of somatropin in human milk. Limited published data indicate that exogenous somatropin does not increase normal breastmilk concentrations of growth hormone. No adverse effects on the breastfed infant have been reported with somatropin. The developmental and health benefits of breastfeeding should be considered along with the mother’s clinical need for NORDITROPIN and any potential adverse effects on the breastfed infant from NORDITROPIN or from the underlying maternal condition.

8.4 Pediatric Use

Safety and effectiveness of NORDITROPIN in pediatric patients have been established in growth failure due to inadequate secretion of endogenous growth hormone, short stature associated with Noonan syndrome, short stature associated with Turner syndrome, short stature in children born small for gestational age (SGA) with no catch-up growth by age 2 years to 4 years of age, idiopathic short stature (ISS), and growth failure due to Prader-Willi syndrome (PWS).

Growth Failure due to Inadequate Secretion of Endogenous Growth Hormone

Safety and effectiveness of NORDITROPIN have been established in pediatric patients with growth failure due to growth hormone deficiency in a multi-center, prospective, randomized, open-label, dose-response study in 111 pediatric patients conducted for a two-year period [see Clinical Studies (14.1)].

Short Stature Associated with Noonan Syndrome

Safety and effectiveness of NORDITROPIN have been established in pediatric patients with Noonan syndrome in a prospective, open-label, randomized, parallel group study in 21 pediatric patients conducted for 2 years [see Clinical Studies (14.2)].

Short Stature Associated with Turner Syndrome

Safety and effectiveness of NORDITROPIN have been established in pediatric patients with short stature associated with Turner syndrome in two randomized, parallel group, open-label, multicenter studies in 87 pediatric patients [see Clinical Studies (14.3)].

Short Stature in Pediatric Patients Born Small for Gestational Age (SGA) with No Catch-up Growth by Age 2 Years to 4 Years of Age

Safety and effectiveness of NORDITROPIN have been established in pediatric patients with short stature born SGA with no catch-up growth in a multi-center, randomized, double-blind, two-arm study to final height in 53 pediatric patients and in a randomized study of 84 prepubertal, non-GHD, Japanese pediatric patients [see Clinical Studies (14.4)].

Idiopathic Short Stature (ISS)

Safety and effectiveness of NORDITROPIN have been established in pediatric patients with ISS based on data from a randomized, open-label clinical study with another somatropin product in 105 pediatric patients [see Clinical Studies (14.5)].

Growth Failure Due to Prader-Willi Syndrome (PWS)

Safety and effectiveness of NORDITROPIN have been established in pediatric patients with growth failure due to Prader-Willi Syndrome based on data from two randomized, open label, controlled clinical trials with another somatropin product in pediatric patients. There have been reports of sudden death after initiating therapy with somatropin in pediatric patients with Prader-Willi syndrome who had one or more of the following risk factors: severe obesity, history of upper airway obstruction or sleep apnea, or unidentified respiratory infection. Male patients with one or more of these factors may be at greater risk than females. Patients with Prader-Willi syndrome should be evaluated for signs of upper airway obstruction and sleep apnea before initiation of treatment with somatropin. [see Contraindications (4), Warnings and Precautions (5.2), Clinical Studies (14.6)].

8.5 Geriatric Use

The safety and effectiveness of NORDITROPIN in patients aged 65 and over has not been evaluated in clinical studies. Elderly patients may be more sensitive to the action of somatropin, and therefore may be more prone to develop adverse reactions. A lower starting dose and smaller dose increments should be considered for older patients [see Dosage and Administration (2.3)].

10 OVERDOSAGE

Short-term overdosage could lead initially to hypoglycemia and subsequently to hyperglycemia. Overdose with somatropin is likely to cause fluid retention. Long-term overdosage could result in signs and symptoms of gigantism and/or acromegaly consistent with the known effects of excess growth hormone.

11 DESCRIPTION

Somatropin is a human growth hormone (GH) produced by recombinant DNA technology using Escherichia Coli. The protein is comprised of 191 amino acids and has a molecular weight of about 22,000 daltons. The amino acid sequence is identical to that of human growth hormone of pituitary origin.

NORDITROPIN (somatropin) injection is a sterile, clear and colorless solution for subcutaneous use in ready-to-administer prefilled single-patient-use pens with a volume of 1.5 mL or 3 mL with a pH of 6.13–6.20.

Each NORDITROPIN contains the following (see Table 3):

Table 3. Contents of NORDITROPIN Pen

Component | 5 mg/1.5 mL | 10 mg/1.5 mL | 15 mg/1.5 mL | 30 mg/3 mL
Somatropin | 5 mg | 10 mg | 15 mg | 30 mg
Histidine | 1 mg | 1 mg | 1.7 mg | 3.3 mg
Mannitol | 60 mg | 60 mg | 58 mg | 117 mg
Phenol | 4.5 mg | 4.5 mg | 4.5 mg | 9 mg
Poloxamer 188 | 4.5 mg | 4.5 mg | 4.5 mg | 9 mg
Hydrochloric acid/sodium hydroxide; to adjust pH | as needed | as needed | as needed | as needed
Water for Injection, USP | up to 1.5 mL | up to 1.5 mL | up to 1.5 mL | up to 3 mL

12 CLINICAL PHARMACOLOGY

12.1 Mechanism of Action

Somatropin binds to dimeric GH receptors located within the cell membranes of target tissue cells. This interaction results in intracellular signal transduction and subsequent induction of transcription and translation of GH-dependent proteins including IGF-1, IGF BP-3 and acid-labile subunit. Somatropin has direct tissue and metabolic effects or mediated indirectly by IGF-1, including stimulation of chondrocyte differentiation, and proliferation, stimulation hepatic glucose output, protein synthesis and lipolysis.

Somatropin stimulates skeletal growth in pediatric patients with GHD as a result of effects on the growth plates (epiphyses) of long bones. The stimulation of skeletal growth increases linear growth rate (height velocity) in most somatropin-treated pediatric patients. Linear growth is facilitated in part by increased cellular protein synthesis.

12.2 Pharmacodynamics

Subcutaneous administration of a single dose of 4 mg NORDITROPIN in healthy subjects (n=26) with suppressed endogenous growth hormone results in an increased mean (SD) IGF-1 level from 190 (46) ng/mL predose to maximal level of 276 (49) ng/mL after approx. 24 hours. After 96 hours, the subjects displayed a mean (SD) IGF-1 concentration of 196 (41) ng/mL, comparable to the predose value.

12.3 Pharmacokinetics

Absorption - Somatropin has been studied following subcutaneous and intravenous administration in adult healthy subjects and GHD patients. A single dose administration of 4 mg NORDITROPIN in healthy subjects (n=26) with suppressed endogenous growth hormone resulted in a mean (SD) Cmax of 34.9 (10.4) ng/mL after approximately 3.0 hours. After a 180-min IV infusion of NORDITROPIN (33 ng/kg/min) administered to GHD patients (n=9), a mean (SD) hGH steady state serum level of approximately 23.1 (15.0) ng/mL was reached at 150 min.

After a SC dose of 0.024 mg/kg or 3 IU/m^2 given in the thigh to adult GHD patients (n=18), mean (SD) Cmax values of 13.8 (5.8) and 17.1 (10.0) ng/mL were observed for the 4 and 8 mg NORDITROPIN vials, respectively, at approximately 4 to 5 hr. post dose. The absolute bioavailability for NORDITROPIN after the SC route of administration is currently not known.

Distribution — The mean (SD) apparent volume of distribution of somatropin after single dose subcutaneous administration of 4 mg NORDITROPIN in healthy subjects is 43.9 (14.9) L.

Elimination

Metabolism — Extensive metabolism studies have not been conducted. The metabolic fate of somatropin involves classical protein catabolism in both the liver and kidneys.

Excretion – The mean apparent terminal T1/2 values in healthy adult subjects (n=26) was 2.0 (0.5) hours. In GHD patients receiving 180-min IV infusion of NORDITROPIN (33 ng/kg/min), a mean clearance rate of approximately 2.3 (1.8) mL/min/kg or 139 (105) mL/min for hGH was observed. Following infusion, serum hGH levels had a biexponential decay with a terminal elimination half-life (T1/2) of approximately 21.1 (5.1) min. The mean apparent terminal T1/2 values in GHD patients receiving a SC dose of 0.024 mg/kg or 3 IU/m^2 was estimated to be approximately 7 to 10 hr. The longer half-life observed after subcutaneous administration is due to slow absorption from the injection site. Urinary excretion of intact somatropin has not been measured.

Geriatric patients — The pharmacokinetics of somatropin have not been studied in patients greater than 65 years of age.

Pediatric patients — The pharmacokinetics of somatropin in pediatric patients are similar to those of adults.

Male and Female Patients — No gender-specific pharmacokinetic studies have been performed with somatropin. The available literature indicates that the pharmacokinetics of somatropin are similar in men and women.

Patients with Renal or Hepatic Impairment — No studies have been performed with somatropin.

12.6 Immunogenicity

The observed incidence of anti-drug antibodies is highly dependent on the sensitivity and specificity of the assay. Differences in assay methods preclude meaningful comparisons of the incidence of anti-drug antibodies in the studies described below with the incidence of anti-drug antibodies in other studies, including those of NORDITROPIN or other somatropins. In the case of growth hormone, antibodies with binding capacities lower than 2 mg/mL have not been associated with growth attenuation. In a very small number of patients treated with somatropin, when binding capacity was greater than 2 mg/mL, interference with the growth response was observed.

In clinical trials, GH deficient pediatric patients receiving NORDITROPIN for up to 12 months were tested for induction of antibodies, and 0 of 358 patients developed antibodies with binding capacities above 2 mg/L. Amongst these patients, 165 had previously been treated with other somatropin formulations, and 193 were previously untreated naive patients. Eighteen of 76 children (~24%) treated with NORDITROPIN for short stature born SGA developed anti-rhGH antibodies.

13 NONCLINICAL TOXICOLOGY

13.1 Carcinogenesis, Mutagenesis, Impairment of Fertility

Carcinogenicity and mutagenicity studies have not been conducted with NORDITROPIN.

In a rat study evaluating female fertility, animals were administered once daily subcutaneous doses of 0.1, 0.3, and 1.1 mg/kg NORDITROPIN beginning two weeks prior to mating, throughout mating and during the first 7 days of pregnancy. Delays in the time to mating were observed at doses greater than or equal to 0.3 mg/kg (approximately 3 times the maximum adult clinical dose of 0.016 mg/kg, based on body surface area), but these doses were also associated with increases in the number of corpora lutea and implantations. A decrease in the pregnancy rate was observed at the dose of 1.1 mg/kg (approximately 10 times the clinical dose of 0.016 mg/kg, based on body surface area). Male fertility parameters have not been evaluated with administration of NORDITROPIN.

14 CLINICAL STUDIES

14.1 Growth Failure due to Inadequate Secretion of Endogenous Growth Hormone

The efficacy and safety of NORDITROPIN was assessed in a multicenter, prospective randomized, open label, dose response study with three doses (0.025, 0.05 and 0.1 mg/kg/day). A total of 111 pediatric patients with GH deficiency were randomized to each dose; 37(0.025 mg/kg/day):38(0.05 mg/kg/day):36(0.1 mg/kg/day). Patients met the following entry criteria: chronological age ≥ 3 years with a skeletal age < 10 years if male and < 8 years if female; pubertal stage = stage 1; previously untreated GH deficiency; peak plasma hormone concentration < 7 ng/ml or < 10 ng/ml (depending on assay used) in two tests.

The results are displayed in Table 4. The adjusted mean increases in HSDS over the 2-year period were 0.81, 1.57 and 1.73 in the 0.025, 0.05 and 0.1 mg/kg/day dose groups, respectively. There was no significant difference in ΔHSDS between the 0.05 and 0.1 mg/kg/day treatment groups. Height velocity (HV, cm/year) and HVSDS increased considerably after initiation of treatment, with the greatest response observed during the first year of treatment.

Table 4 – Efficacy of NORDITROPIN in Pediatric GH Deficiency

 | NORDITROPIN
 | 0.025 mg/kg/day |  |  | 0.05 mg/kg/day |  |  | 0.1 mg/kg/day
 | N | Mean | SD | N | Mean | SD | N | Mean | SD
Change in Standing Height (cm)
Baseline to Month 12 | 37 | 9.5 | 2.1 | 37 | 13.2* | 2.6 | 34 | 13.7* | 2.7
Baseline to Month 24 | 34 | 17.6 | 3.4 | 37 | 22.2* | 4.7 | 33 | 23.7* | 4.0
Change in Sitting Height (cm)
Baseline to Month 12 | 32 | 5.4 | 2.4 | 36 | 6.5* | 1.6 | 32 | 7.4** | 1.5
Baseline to Month 24 | 29 | 9.3 | 2.5 | 35 | 10.8** | 2.6 | 31 | 12.2** | 2.0
Change in Bone Age (yr)
Baseline to Month 12 | 37 | 1.3 | 0.9 | 38 | 1.7 | 0.8 | 34 | 1.6 | 0.8
Month 12 to Month 24 | 37 | 0.6 | 2.5 | 38 | 1.4 | 2.7 | 34 | 1.6* | 0.8

*Significant (p <0.05) change from baseline compared to the 0.025 mg/kg/group

**Significant (p <0.05) change from baseline compared to both other groups

14.2 Short Stature Associated with Noonan Syndrome

A prospective, open label, randomized, parallel group study with 21 pediatric patients was conducted for 2 years to evaluate the efficacy and safety of NORDITROPIN. Additional 6 children were not randomized, but did follow the protocol. Inclusion criteria included bone age determination showing no significant acceleration, prepubertal status, height SDS <-2, and HV SDS <1 during the 12 months pre-treatment. Exclusion criteria were previous or ongoing treatment with growth hormone, anabolic steroids or corticosteroids, congenital heart disease or other serious disease perceived to possibly have major impact on growth, FPG >6.7 mmol/L (>120 mg/dL), or growth hormone deficiency (peak GH levels <10 ng/mL). The twenty-four, 12 female and 12 male, patients 3 – 14 years of age received either 0.033 mg/kg/day or 0.066 mg/kg/day of NORDITROPIN subcutaneously which was adjusted based on growth response after the first 2 years.

After the initial two-year study, NORDITROPIN treatment continued until final height. Retrospective final height was collected from 18 patients in the study and the 6 who had followed the protocol without randomization. Historical reference materials of height velocity and adult height analyses of Noonan patients served as the controls.

Patients obtained a final height (FH) gain from baseline of 1.5 and 1.6 SDS estimated according to the national and the Noonan reference, respectively. A height gain of 1.5 SDS (national) corresponds to a mean height gain of 9.9 cm in boys and 9.1 cm in girls at 18 years of age, while a height gain of 1.6 SDS (Noonan) corresponds to a mean height gain of 11.5 cm in boys and 11.0 cm in girls at 18 years of age.

A comparison of HV between the two treatment groups during the first two years of treatment for the randomized subjects was 10.1 and 7.6 cm/year with 0.066 mg/kg/day versus 8.55 and 6.7 cm/year with 0.033 mg/kg/day, for Year 1 and Year 2, respectively.

14.3 Short Stature Associated with Turner Syndrome

Two randomized, parallel group, open label, multicenter studies were conducted in the Netherlands to evaluate the efficacy and safety of NORDITROPIN. Patients were treated to final height in both studies [height velocity (HV) < 2 cm/year]. Changes in height were expressed as standard deviation scores (SDS) utilizing reference data for untreated Turner syndrome patients as well as the national Dutch population.

In Study 1, 68 euthyroid Caucasian patients stratified based on age and baseline height SDS were randomized in a 1:1:1 ratio to three different NORDITROPIN treatment regimens: 0.045 mg/kg/day (Dose A) for the entire study; 0.045 mg/kg/day for the first year and 0.067 mg/kg/day thereafter (Dose B); or 0.045 mg/kg/day for the first year, 0.067 for the second year, and 0.089 mg/kg/day thereafter (Dose C). At baseline, mean age was 6.5 years, mean height SDS (National standard) was -2.7, and mean HV during the previous year was 6.5 cm/year. Patients also received estrogen therapy after age 12 and following four years of NORDITROPIN treatment if they did not have spontaneous puberty.

Patients were treated for a mean of 8.4 years. As seen in Table 5, overall mean final height was 161 cm in the 46 children who attained final height. Seventy percent of these children reached a final height within the normal range (height SDS > -2 using the National standard). A greater percentage of children in the two escalated dose groups reached normal final height. The mean changes from baseline to final height in height SDS after treatment with Dose B and Dose C were significantly greater than the mean changes observed after treatment with Dose A (utilizing both the National and Turner standards). The mean changes from baseline to final height in height SDS (Turner standard) in Table 5 correspond to mean height gains of 9.4, 14.1 and 14.4 cm after treatment with Doses A, B and C, respectively. The mean changes from baseline to final height in height SDS (National standard) in Table 5 correspond to mean height gains of 4.5, 9.1 and 9.4 cm after treatment with Doses A, B and C, respectively. In each treatment group, peak HV was observed during treatment Year 1, and then gradually decreased each year; during Year 4, HV was less than the pre-treatment HV. However, between Year 2 and Year 6, a greater HV was observed in the two dose escalation groups compared to the 0.045 mg/kg/day group.

Table 5 – Final Height-Related Results After Treatment of Patients with Turner Syndrome with NORDITROPIN in a Randomized, Dose Escalating Study

 | Dose A; 0.045 mg/kg/day; (n = 19) | Dose B; up to 0.067 mg/kg/day; (n = 15) | Dose C; up to 0.089 mg/kg/day; (n = 12) | Total; (n = 46)
Baseline height (cm)^1 | 105 (12) | 108 (12.7) | 107 (11.7) | 106 (11.9)
Final height (cm)^1 | 157 (6.7) | 163 (6.0) | 163 (4.9) | 161 (6.5)
Number (%) of patients reaching normal height (height SDS >-2 using National standard) | 10 (53%) | 12 (80%) | 10 (83%) | 32 (70%)
Height SDS (Turner standard)^2
Final [95% CI] | 1.7 [1.4, 2.0] | 2.5 [2.1, 2.8]^3 | 2.5 [2.1, 2.9]^4 | NA
Change from baseline [95% CI] | 1.5 [1.2, 1.8] | 2.2 [1.9, 2.5]^3 | 2.2 [1.9, 2.6]^4 | NA
Height SDS (National standard)^2
Final [95% CI] | -1.9 [-2.2, -1.6] | -1.2 [-1.5, -0.9]^4 | -1.2 [-1.6, -0.8]^5 | NA
Change from baseline [95% CI] | 0.7 [0.4, 1.0] | 1.4 [1.1, 1.7]^4 | 1.4 [1.1, 1.8]^5 | NA

Values are expressed as mean (SD) unless otherwise indicated. SDS: Standard deviation score.

^1Unadjusted (raw) means; ^2Adjusted (least squares) means based on an ANCOVA model including terms for treatment,

duration of treatment, age at baseline, bone age at baseline, height SDS at baseline, age at onset of puberty and mid-parental target height SDS;

^3p=0.005 vs. Dose A; ^4p=0.006 vs. Dose A; ^5p=0.008 vs. Dose A

In Study 2, 19 euthyroid Caucasian patients (with bone age ≤13.9 years) were randomized to treatment with 0.067 mg/kg/day of NORDITROPIN as a single subcutaneous dose in the evening, or divided into two doses (1/3 morning and 2/3 evening). All subjects were treated with concomitant ethinyl estradiol. Overall, at baseline, mean age was 13.6 years, mean height SDS (National standard) was -3.5 and mean HV during the previous year was 4.3 cm/year. Patients were treated for a mean of 3.6 years. In that there were no significant differences between the two treatment groups for any linear growth variables, the data from all patients were pooled. Overall mean final height was 155 cm in the 17 children who attained final height. Height SDS changed significantly from -3.5 at baseline to -2.4 at final height (National standard), and from 0.7 to 1.3 at final height (Turner standard).

14.4 Short Stature in Pediatric Patients Born Small for Gestational Age (SGA) with No Catch-up Growth by Age 2-4 Years

A multi-center, randomized, double-blind, two-arm study to final height (Study 1) and a 2-year, multi-center, randomized, double-blind, parallel-group study (Study 2) were conducted to assess the efficacy and safety of NORDITROPIN. Changes in height and height velocity were compared to a national reference population in both studies.

Study 1 included 53, 38 male, 15 female, non-GHD, Dutch prepubertal pediatric patients 3-11 years of age with short stature born SGA with no catch-up growth. Catch-up growth was defined as obtaining a height of ≥ 3rd percentile within the first 2 years of life or at a later stage. Inclusion criteria included: birth length < 3rd percentile for gestational age, and height velocity (cm/year) for chronological age < 50th percentile. Exclusion criteria included chromosomal abnormalities, signs of a syndrome (except for Silver-Russell syndrome), serious/chronic co-morbid disease, malignancy, and previous rhGH therapy. NORDITROPIN was administered subcutaneously daily at bedtime at a dose of approximately 0.033 (Dose A) or 0.067 mg/kg/day (Dose B) for the entire treatment period. Final height was defined as a height velocity below 2 cm/year. Treatment with NORDITROPIN was continued to final height for up to 13 years. Mean duration of treatment was 9.5 years (boys) and 7.9 years (girls).

38 out of 53 children (72%) reached final height. Sixty-three percent (24 out of 38) of the children who reached final height were within the normal range of their healthy peers (Dutch national reference). For both doses combined, actual mean final height was 171 (SD 6.1) cm in boys and 159 (SD 4.3) cm in girls.

As seen in Table 6, for boys and girls combined, both mean final height SDS, and increase in height SDS from baseline to final height, were significantly greater after treatment with Dose B (0.067 mg/kg/day). A similar dose response was observed for the increase in height SDS from baseline to Year 2 (Table 6).

Overall mean height velocity at baseline was 5.4 cm/y (SD 1.2; n=29). Height velocity was greatest during the first year of NORDITROPIN treatment and was significantly greater after treatment with Dose B (mean 11.1 cm/y [SD 1.9; n=19]) compared with Dose A (mean 9.7 cm/y [SD 1.3; n=10]).

Table 6 – Study 1: Results for Final Height SDS and Change from Baseline to Final Height in Height SDS Using National Standard After Long-Term Treatment of SGA Children with NORDITROPIN

 | Raw Mean ± SD (N)
 | Dose A; 0.033 mg/kg/day | Dose B; 0.067 mg/kg/day | Total
Baseline Height SDS | -3.2 ± 0.7 (26) | -3.2 ± 0.7 (27) | -3.2 ± 0.7 (53)
Adjusted least-squares mean ± standard error (N), Treatment Difference [95% confidence intervals]
Height SDS: Change from Baseline at Year 2^2 | 1.4 ± 0.1 (26) | 1.8 ± 0.1 (26) | Treatment Diff = 0.4; [0.2, 0.7]^3
Height SDS: Change from Baseline at Final Height^1 | 1.4 ± 0.2 (19) | 1.8 ± 0.2 (19) | Treatment Diff = 0.5; [0.0, 0.9]^3
Final Height SDS^1 | -1.8 ± 0.2 (19) | -1.3 ± 0.2 (19) | Treatment Diff = 0.5; [0.0, 0.9]^3
Final Height SDS > -2 | 13/19 (68%) | 11/19 (58%) | 24/38 (63%)

SDS: Standard deviation score.

^1Adjusted (least-squares) means based on an ANCOVA model including terms for treatment, gender, age at baseline, bone age at baseline, height SDS at baseline, duration of treatment, peak GH after stimulation and baseline IGF-1.

^2 Adjusted (least-squares) means based on an ANCOVA model including terms for treatment, gender, age at baseline, height SDS at baseline, and pubertal status.

^3 p<0.05

In study 2, 84 randomized, prepubertal, non-GHD, Japanese children (age 3-8) were treated for 2 years with 0.033 or 0.067 mg/kg/day of NORDITROPIN subcutaneously daily at bedtime or received no treatment for 1 year. Additional inclusion criteria included birth length or weight SDS ≤ -2 or < 10th percentile for gestational age, height SDS for chronological age ≤ -2, and height velocity SDS for chronological age < 0 within one year prior to Visit 1. Exclusion criteria included diabetes mellitus, history or presence of active malignancy, and serious co-morbid conditions.

As seen in Table 7, for boys and girls combined, there was a dose-dependent increase in height SDS at Year 1 and Year 2. The increase in height SDS from baseline to Year 2 (0.033 mg/kg/day, 0.8 vs. 0.067 mg/kg/day, 1.4) was significantly greater after treatment with 0.067 mg/kg/day. In addition, the increase in height SDS at Year 1 was significantly greater in both active treatment groups compared to the untreated control group.

Table 7 – Study 2: Results for Change from Baseline in Height SDS At Year 1 and Year 2 Using National Standard After Short-Term Treatment of SGA Children with NORDITROPIN

 | Raw Mean ± SD (N)
 | No Treatment | 0.033 mg/kg/day | 0.067 mg/kg/day
Height SDS: Baseline | -2.9 ± 0.5 (15) | -3.0 ± 0.6 (35) | -2.9 ± 0.7 (34)
Height SDS: Year 1 | -2.8 ± 0.5 (15) | -2.4 ± 0.6 (33) | -2.0 ± 0.8 (34)
Height SDS: Year 2 | NA | -2.2 ± 0.7 (33) | -1.4 ± 0.7 (32)
Adjusted least-squares mean ± standard error (N), Treatment Diff
[95% confidence intervals]
Height SDS: Change from Baseline at Year 1^1 | 0.1 ± 0.1 (15) | 0.6 ± 0.1 (33) | 0.9 ± 0.1 (34)
Height SDS: Change from Baseline at Year 1^1 | 0.033 vs. No Treatment: Treatment Diff = 0.5, [0.3, 0.7]^2; 0.067 vs. No Treatment: Treatment Diff = 0.8, [0.6, 1.0]^2; 0.067 vs. 0.033: Treatment Diff = 0.3, [0.2, 0.5]^2
Height SDS: Change from Baseline at Year 2^1 | NA | 0.8 ± 0.1 (33) | 1.4 ± 0.1 (32)
Height SDS: Change from Baseline at Year 2^1 | 0.067 vs. 0.033: Treatment Diff = 0.6, [0.5, 0.8], p-value < 0.0001

SDS: Standard deviation score.

^1Adjusted (least-squares) means based on an ANCOVA model including terms for treatment, gender, age at baseline, and height SDS at baseline. All children remained prepubertal during the study.

^2 p< 0.0001

14.5 Idiopathic Short Stature (ISS)

The efficacy and safety of another somatropin product was evaluated in 105 patients who were retrospectively identified as having ISS in a randomized, open-label, clinical study. Patients were enrolled on the basis of short stature, stimulated GH secretion > 10 ng/mL, and prepubertal status. All patients were observed for height progression for 12 months and were subsequently randomized to this other somatropin product or observation only and followed to final height. Two doses of this other somatropin product were evaluated in this trial: 0.23 mg/kg/week (0.033 mg/kg/day) and 0.47 mg/kg/week (0.067 mg/kg/day). Baseline patient characteristics for the ISS patients who remained prepubertal at randomization (n= 105) were: mean (± SD): chronological age 11.4 (1.3) years, height SDS -2.4 (0.4), height velocity SDS -1.1 (0.8), and height velocity 4.4 (0.9) cm/yr, IGF-1 SDS -0.8 (1.4). Patients were treated for a median duration of 5.7 years. Results for final height SDS are displayed by treatment arm in Table 8. The observed mean gain in final height was 9.8 cm for females and 5.0 cm for males for both doses combined compared to untreated control subjects. A height gain of 1 SDS was observed in 10% of untreated subjects, 50% of subjects receiving 0.23 mg/kg/week and 69% of subjects receiving 0.47 mg/kg/week.

Table 8 – Final height SDS results for pre-pubertal patients with ISS*

 |  | Another Somatropin Product
 | Untreated; (n=30) | 0.033 mg/kg/day; (n=30) | 0.067 mg/kg/day; (n=42) | 0.033 vs Untreated; (95% CI) | 0.067 vs Untreated; (95% CI)
Baseline height SDS; Final height SDS minus baseline | 0.41 (0.58) | 0.95 (0.75) | 1.36 (0.64) | +0.53 (0.20, 0.87)** | +0.94 (0.63, 1.26)**
Baseline predicted ht; Final height SDS minus baseline predicted final height SDS | 0.23 (0.66) | 0.73 (0.63) | 1.05 (0.83) | +0.60 (0.09, 1.11)** | +0.90 (0.42, 1.39)**

Least square means based on ANCOVA (final height SDS and final height SDS minus baseline predicted height SDS were adjusted for baseline height SDS)

* Mean (SD) are observed values

**p<0.05

14.6 Growth Failure Due to Prader-Willi Syndrome (PWS)

The safety and efficacy of another somatropin product were evaluated in two randomized, open-label, controlled clinical studies. Patients received either this other somatropin product or no treatment for the first year of the studies, while all patients received this other somatropin product during the second year. This other somatropin product was administered as a daily SC injection, and the dose was calculated for each patient every 3 months. In Study 1, the treatment group received this other somatropin product at a dose of 0.24 mg/kg/week during the entire study. During the second year, the control group received this other somatropin product at a dose of 0.48 mg/kg/week. In Study 2, the treatment group received this other somatropin product at a dose of 0.36 mg/kg/week during the entire study. During the second year, the control group received this other somatropin product at a dose of 0.36 mg/kg/week.

The results are presented in Table 9. Linear growth continued to increase in the second year, when both groups received treatment with this other somatropin product.

Table 9 – Efficacy of Another Somatropin Product in Pediatric Patients with Prader-Willi Syndrome (Mean ± SD)
 | Study 1 |  | Study 2
 | Another Somatropin Product (0.24 mg/kg/week); (n=15) | Untreated Control (n=12) | Another Somatropin Product (0.36 mg/kg/week); (n=7) | Untreated Control; (n=9)
Linear growth (cm); Baseline height | 112.7 ± 14.9 | 109.5 ± 12.0 | 120.3 ± 17.5 | 120.5 ± 11.2
Growth from 0 to 12 months | 11.6* ± 2.3 | 5.0 ± 1.2 | 10.7* ± 2.3 | 4.3 ± 1.5
Baseline SDS | -1.6 ± 1.3 | -1.8 ± 1.5 | -2.6 ± 1.7 | -2.1 ± 1.4
SDS at 12 months | -0.5* ± 1.3 | -1.9 ± 1.4 | -1.4* ± 1.5 | -2.2 ± 1.4

* p <0.05

14.7 Adults with Growth Hormone Deficiency (GHD)

A total of six randomized, double-blind, placebo-controlled studies were performed. Two representative studies, one in adult onset (AO) GHD patients and a second in childhood onset (CO) GHD patients, are described below.

Study 1

A single center, randomized, double-blind, placebo-controlled, parallel-group, six month clinical trial was conducted in 31 adults with AO GHD comparing the effects of NORDITROPIN (somatropin) injection and placebo on body composition. Patients in the active treatment arm were treated with NORDITROPIN 0.017 mg/kg/day (not to exceed 1.33 mg/day). The changes from baseline in lean body mass (LBM) and percent total body fat (TBF) were measured by total body potassium (TBP) after 6 months.

Treatment with NORDITROPIN produced a significant increase from baseline in LBM compared to placebo (Table 10).

Table 10 – Lean Body Mass (kg) by TBP

 | NORDITROPIN; (n=15) | Placebo; (n=16)
Baseline (mean) | 50.27 | 51.72
Change from baseline at 6 months (mean) | 1.12 | -0.63
Treatment difference (mean); 95% confidence interval; p-value | 1.74; (0.65, 2.83); p=0.0028*

*Least square mean based on an ANOVA model including treatment and sex as factors

Analysis of the treatment difference on the change from baseline in percent TBF revealed a significant decrease in the NORDITROPIN-treated group compared to the placebo group (Table 11).

Table 11 – Total Body Fat (%) by TBP

 | NORDITROPIN; (n=15) | Placebo; (n=16)
Baseline (mean) | 44.74 | 42.26
Change from baseline at 6 months (mean) | -2.83 | 1.92
Treatment difference (mean); 95% confidence interval; p-value | -4.74; (-7.18, -2.30); p=0.0004*

*Least square mean based on an ANOVA model including treatment and sex as factors

NORDITROPIN also significantly increased serum osteocalcin (a marker of osteoblastic activity).

Study 2

A single center, randomized, double-blind, placebo-controlled, parallel-group, dose-finding, six month clinical trial was conducted in 49 men with CO GHD comparing the effects of NORDITROPIN and placebo on body composition. Patients were randomized to placebo or one of three active treatment groups (0.008, 0.016, and 0.024 mg/kg/day). Thirty three percent of the total dose to which each patient was randomized was administered during weeks 1-4, 67% during weeks 5-8, and 100% for the remainder of the study. The changes from baseline in LBM and percent TBF were measured by TBP after 6 months.

Treatment with NORDITROPIN produced a significant increase from baseline in LBM compared to placebo (pooled data) (Table 12).

Table 12 – Lean Body Mass (kg) by TBP

 | NORDITROPIN; (n=36) | Placebo; (n=13)
Baseline (mean) | 48.18 | 48.90
Change from baseline at 6 months (mean) | 2.06 | 0.70
Treatment difference (mean); 95% confidence interval; p-value | 1.40; (0.39, 2.41); p=0.0079*

*Least square mean based on an ANOVA model including treatment as a factor

Analysis of the treatment difference on the change from baseline in percent TBF revealed a significant decrease in the NORDITROPIN-treated groups (pooled data) compared to the placebo group (Table 13).

Table 13 – Total Body Fat (%) by TBP

 | NORDITROPIN; (n=36) | Placebo; (n=13)
Baseline (mean) | 34.55 | 34.07
Change from baseline at 6 months (mean) | -6.00 | -1.78
Treatment difference (mean); 95% confidence interval; p-value | -4.24; (-7.11, -1.37); p=0.0048*

*Least square mean based on an ANOVA model including treatment as a factor

16 HOW SUPPLIED/STORAGE AND HANDLING

NORDITROPIN (somatropin) injection is a clear and colorless solution available as FlexPro single-patient-use prefilled pens:

- NORDITROPIN FlexPro 5 mg/1.5 mL (orange) NDC 0169-7704-21
- NORDITROPIN FlexPro 10 mg/1.5 mL (blue) NDC 0169-7705-21
- NORDITROPIN FlexPro 15 mg/1.5 mL (green) NDC 0169-7708-21
- NORDITROPIN FlexPro 30 mg/3 mL (purple) NDC 0169-7703-21

NORDITROPIN 5 mg/1.5 mL, 10 mg/1.5 mL, and 15 mg/1.5 mL FlexPro pens are compatible with FlexPro PenMate. The FlexPro PenMate is an accessory device that is dispensed separately with its enclosed Instructions for Use.

NORDITROPIN 30 mg/3 mL FlexPro pen is not compatible with FlexPro PenMate.

Each NORDITROPIN FlexPro pen is for use by a single patient. A NORDITROPIN FlexPro pen must never be shared between patients, even if the needle is changed.

Unused NORDITROPIN FlexPro prefilled pens must be stored refrigerated at 2°C to 8°C (36°F to 46°F). Do not store directly adjacent to the refrigerator cooling element. Do not freeze. Avoid direct light.

Table 14 – Storage Conditions and Expiration

Before Use | In-use (After 1st injection)
Storage; requirement | Storage Option 1; (Refrigeration) | Storage Option 2; (Room temperature)
2ºC to 8ºC; (36ºF to 46ºF); Until exp. date | 2ºC to 8ºC; (36ºF to 46ºF); 4 weeks | Up to 25ºC (77ºF); 3 weeks

17 PATIENT COUNSELING INFORMATION

Advise the patient to read the FDA-approved patient labeling (Patient Information and Instructions for Use).

- Neoplasms – Advise childhood cancer survivors/caregivers that individuals treated with brain/head radiation are at increased risk of secondary neoplasms and as a precaution need to be monitored for recurrence. Advise patients/caregivers to report marked changes in behavior, onset of headaches, vision disturbances and/or changes in skin pigmentation or changes in the appearance of pre-existing nevi.
- Fluid Retention - Advise patients that fluid retention during NORDITROPIN replacement therapy in adults may frequently occur. Inform patients of the clinical manifestations of fluid retention (e.g. edema, arthralgia, myalgia, nerve compression syndromes including carpal tunnel syndrome/paraesthesias) and to report to their healthcare provider any of these signs or symptoms occur during treatment with NORDITROPIN.
- Pancreatitis - Advise patients/caregivers that pancreatitis may develop and to report to their healthcare provider any new onset abdominal pain.
- Hypoadrenalism - Advise patients/caregivers who have or who are at risk for pituitary hormone deficiency(s) that hypoadrenalism may develop and to report to their healthcare provider if they experience hyperpigmentation, extreme fatigue, dizziness, weakness, or weight loss.
- Hypothyroidism - Advise patients/caregivers that undiagnosed/untreated hypothyroidism may prevent an optimal response to NORDITROPIN. Advise patients/caregivers they may require periodic thyroid function tests.
- Intracranial Hypertension - Advise patients/caregivers to report to their healthcare provider any visual changes, headache, and nausea and/or vomiting.
- Hypersensitivity Reactions – Advise patients/caregivers that serious systemic hypersensitivity reactions (anaphylaxis and angioedema) are possible and that prompt medical attention should be sought if an allergic reaction occurs.
- Glucose Intolerance/ Diabetes Mellitus – Advise patients/caregivers that new onset impaired glucose intolerance/diabetes mellitus or exacerbation of preexisting diabetes mellitus can occur and monitoring of blood glucose during treatment with NORDITROPIN may be needed.

NORDITROPIN® and FlexPro® are registered trademarks of Novo Nordisk Health Care AG.

Novo Nordisk is a registered trademark of Novo Nordisk A/S.

PATENT Information: http://novonordisk-us.com/products/product-patents.html

Manufactured by:

Novo Nordisk Inc.

800 Scudders Mill Road

Plainsboro, NJ 08536 USA

U.S. License No. 1261

For information about
NORDITROPIN call:
1 (888) 668-6444

© 2025 Novo Nordisk A/S

Patient Package Insert

PATIENT INFORMATION

NORDITROPIN® (nor-dee-tro-pin)

(somatropin) injection for subcutaneous use

What is NORDITROPIN?

NORDITROPIN is a prescription medicine that contains human growth hormone, the same growth hormone made by the human body.

NORDITROPIN is given by injection under the skin (subcutaneous) and is used to treat:

- children who are not growing because of low or no growth hormone.
- children who are short (in stature) and who have Noonan syndrome, Turner syndrome, or were born small (small for gestational age-SGA) and have not caught-up in growth by age 2 to 4 years.
- children who have Idiopathic Short Stature (ISS).
- children who are not growing who have Prader-Willi syndrome (PWS).
- adults who do not make enough growth hormone.

Do not use NORDITROPIN if:

- you have a critical illness caused by certain types of heart or stomach surgery, trauma or breathing (respiratory) problems.
- you are a child with Prader-Willi syndrome who is severely obese or has breathing problems including sleep apnea (briefly stop breathing during sleep).
- you have cancer or other tumors.
- you are allergic to somatropin or any of the ingredients in NORDITROPIN. See the end of this leaflet for a complete list of ingredients in NORDITROPIN.
- your healthcare provider tells you that you have certain types of eye problems caused by diabetes (diabetic retinopathy).
- you are a child with closed bone growth plates (epiphyses).

Before taking NORDITROPIN, tell your healthcare provider about all of your medical conditions, including if you:

- have had heart or stomach surgery, trauma or serious breathing (respiratory) problems.
- have had a history of problems breathing while you sleep (sleep apnea).
- have or have had cancer or any tumor.
- have diabetes.
- are pregnant or plan to become pregnant. It is not known if NORDITROPIN will harm your unborn baby. Talk to your healthcare provider if you are pregnant or plan to become pregnant.
- are breastfeeding or plan to breastfeed. It is not known if NORDITROPIN passes into your breast milk. You and your healthcare provider should decide if you will take NORDITROPIN while you breastfeed.

Tell your healthcare provider about all the medicines you take, including prescription and over-the-counter medicines, vitamins, and herbal supplements. NORDITROPIN may affect how other medicines work, and other medicines may affect how NORDITROPIN works.

How should I use NORDITROPIN?

- Read the detailed Instructions for Use that come with NORDITROPIN.
- NORDITROPIN comes in 4 different dosage strengths. Your healthcare provider will prescribe the dose that is right for you.
- Your healthcare provider will show you how to inject NORDITROPIN.
- Use NORDITROPIN exactly as your healthcare provider tells you to.
  - NORDITROPIN FlexPro pens are for use by 1 person only.
  - Do not share your NORDITROPIN pens and needles with another person, even if the needle has been changed. You may give another person an infection or get an infection from them.

What are the possible side effects of NORDITROPIN?

NORDITROPIN may cause serious side effects, including:

- high risk of death in people who have critical illnesses because of heart or stomach surgery, trauma or serious breathing (respiratory) problems.
- high risk of sudden death in children with Prader-Willi syndrome who are severely obese or have breathing problems, including sleep apnea.
- increased risk of growth of cancer or a tumor that is already present and increased risk of the return of cancer or a tumor in people who were treated with radiation to the brain or head as children and who developed low growth hormone problems. Your or your child’s healthcare provider will need to monitor you or your child for a return of cancer or a tumor. Contact the healthcare provider if you or your child starts to have headaches, or have changes in behavior, changes in vision, or changes in moles, birthmarks, or the color of your skin.
- new or worsening high blood sugar (hyperglycemia) or diabetes. Your or your child’s blood sugar may need to be monitored during treatment with NORDITROPIN.
- increase in pressure in the skull (intracranial hypertension). If you or your child has headaches, eye problems, nausea or vomiting, contact the healthcare provider.
- serious allergic reactions. Get medical help right away if you or your child has the following symptoms:
- swelling of your face, lips, mouth, or tongue
- trouble breathing
- wheezing
- severe itching
- skin rashes, redness, or swelling
- dizziness or fainting
- fast heartbeat or pounding in your chest
- sweating
- your body holding too much fluid (fluid retention) such as swelling in the hands and feet, pain in your joints or muscles or nerve problems that cause pain, burning or tingling in the hands, arms, legs and feet. Fluid retention can happen in adults during treatment with NORDITROPIN. Tell your healthcare provider if you have any of these signs or symptoms of fluid retention.
- decrease in a hormone called cortisol. The healthcare provider will do blood tests to check your or your child’s cortisol levels. Tell your or your child’s healthcare provider if you or your child has darkening of the skin, severe fatigue, dizziness, weakness, or weight loss.
- decrease in thyroid hormone levels. Decreased thyroid hormone levels may affect how well NORDITROPIN works. The healthcare provider will do blood tests to check your or your child’s thyroid hormone levels.
- hip and knee pain or a limp in children (slipped capital femoral epiphysis). This may lead to a serious condition where bone tissue dies due to a lack of blood supply (osteonecrosis). Get medical help for your child right away if your child develops a limp or has hip or knee pain.
- worsening of curvature of the spine (scoliosis).
- severe and constant abdominal pain. This could be a sign of pancreatitis. Tell your or your child’s healthcare provider if you or your child has any new abdominal pain.
- loss of fat and tissue weakness in the area of skin you inject. Talk to your healthcare provider about rotating the areas where you inject NORDITROPIN.
- increase in phosphorus, alkaline phosphatase and parathyroid hormone levels in your blood. Your or your child’s healthcare provider will do blood tests to check this.

The most common side effects of NORDITROPIN include:

- injection site reactions and rashes
- headaches

These are not all the possible side effects of NORDITROPIN.

Call your doctor for medical advice about side effects. You may report side effects to FDA at 1-800-FDA-1088. You may also report side effects to Novo Nordisk at 1-888-668-6444.

How should I store NORDITROPIN?

- Before you use NORDITROPIN FlexPro pens for the first time:
- Store your new, unused NORDITROPIN pen in a refrigerator between 36ºF to 46ºF (2ºC to 8ºC).
- Do not freeze NORDITROPIN.
- When stored in the refrigerator, do not store NORDITROPIN directly next to the cooling element.
- Keep NORDITROPIN away from direct light.
- Do not use NORDITROPIN that has been frozen or in temperatures warmer than 77ºF (25ºC).
- Do not use NORDITROPIN after the expiration date printed on the carton and the pen.
- After you use NORDITROPIN FlexPro pens and there is still medicine left:
- Store remaining NORDITROPIN in the refrigerator between 36ºF to 46ºF (2ºC to 8ºC) and use within 4 weeks, or
- Store remaining NORDITROPIN at room temperature no warmer than 77ºF (25ºC) and use within 3 weeks.

Keep NORDITROPIN and all medicines out of the reach of children.

General information about the safe and effective use of NORDITROPIN.

Medicines are sometimes prescribed for purposes other than those listed in a Patient Information leaflet. Do not use NORDITROPIN for a condition for which it was not prescribed. Do not give NORDITROPIN to other people, even if they have the same symptoms that you have. It may harm them. You can ask your pharmacist or healthcare provider for information about NORDITROPIN that is written for health professionals.

What are the ingredients in NORDITROPIN?

Active ingredient: somatropin

Inactive ingredients: Histidine, Mannitol, Phenol, Poloxamer 188, Hydrochloric Acid/Sodium Hydroxide (as needed) and Water for Injection

Manufactured by: Novo Nordisk Inc.
Plainsboro, NJ 08536

U.S. License No. 1261

This Patient Information has been approved by the U.S. Food and Drug Administration. Revised: 07/2025

Instructions for Use – 5mg

NORDITROPIN® [nor-dee-tro-pin]
(somatropin)
injection, for subcutaneous use
5mg

Norditropin FlexPro Pen is for single-patient-use only.

Supplies you will need:

- Norditropin FlexPro prefilled Pen
  new injection needle. Norditropin prefilled Pen is designed to be used with all Novo Nordisk disposable needles up to a length of 8 mm
- sharps disposal container. See step 5 for information on how to throw away (dispose of) used needles and Pens.
- alcohol pad
- gauze pad

How to use your Norditropin FlexPro Pen

5 steps you should follow for a Norditropin injection:

Step 1: Prepare your Norditropin FlexPro Pen
Step 2: Check the Norditropin flow with each new Pen
Step 3: Select your dose
Step 4: Inject your dose
Step 5: After your injection

For further information about your Pen see:

Frequently Asked Questions
Important information
Patient Information
ꜝImportant information
Make sure that you read this information carefully.
ꜟAdditional information

Norditropin is for use under the skin only (subcutaneous).

Do not share your Norditropin Pen and needles with another person. You may give another person an infection or get an infection from them.

Do not use your Pen without proper training from your healthcare provider.

Make sure that you are confident in giving an injection with the Pen before you start your treatment.

If you are blind or have poor eyesight and cannot read the dose counter on the Pen, do not use this Pen without help. Get help from a person with good eyesight who is trained to use the Pen.

Step 1. Prepare your Norditropin FlexPro Pen

- Wash your hands with soap and water.
  1. Check the name, strength, and colored label on your Pen to make sure that it contains Norditropin in the right strength.
  1. Pull off the Pen cap.
  1. Turn the Pen upside down 1 or 2 times to check that the Norditropin in your Pen is clear and colorless.
See figure A. If the Norditropin looks cloudy, do not use the Pen.

- When you are ready to give your injection, take a new disposable needle, and remove the paper tab.
- Push the needle straight onto the Pen. Turn the needle clockwise until it is on tight. See figure B.

ꜝAlways use a new needle for each injection. This reduces the risk of contamination, infection, leakage of Norditropin, and blocked needles leading to incorrect dosing.

- Pull off the outer needle cap and dispose of it. See figure C.

- Pull off the inner needle cap and dispose of it. See figure D.
ꜟA drop of Norditropin may appear at the needle tip. This is normal, but you must still check the Norditropin flow with each new Pen. See step 2.

ꜝNever use a bent or damaged needle.

Step 2. Check the Norditropin flow with each new Pen

ꜟIf your Pen is already in use, go to step 3.

Before using a new Pen, check the Norditropin flow to make sure the growth hormone can flow through the Pen and needle.

1. Turn the dose selector clockwise 1 tick marking on the dose counter to select 0.025 mg. You will hear a faint “click” when you turn the dose selector. See figure E.

- 1 marking on the dose counter equals 0.025 mg. See figure F.

- Hold the Pen with the needle pointing up. Press and hold in the dose button until the dose counter returns to “0”. The “0” must line up with the dose pointer. See figure G.

- Check that a drop of Norditropin appears at the needle tip. See figure H.

ꜝIf no Norditropin appears, repeat step 2 up to 6 times.

If you still do not see a drop of Norditropin, change the needle:

1. Carefully remove the needle from the Pen by turning the needle counterclockwise. Place the needle in a sharps disposal container immediately. See step 5.
2. and repeat step 2 again.
Do not use the Pen if a drop of Norditropin still does not appear after changing the needle and repeating step 2. Call Novo Nordisk at
1-888-668-6444 for help.

Step 3. Select your dose

- To start, check that the dose pointer is set at “0”.
- • Turn the dose selector clockwise to select the dose you need. See figure I.
When you have selected your dose, you can go to step 4.

ꜟIf there is not enough Norditropin left to select a full dose, see Frequently Asked Questions.

ꜟThe dose counter shows the dose in “mg“. See figures J and K. Always use the dose counter to select the exact dose. Do not use the “click“ sounds you hear when you turn the dose selector or the Pen scale to select your dose. Only the dose pointer on the dose counter will show the exact dose selected.

ꜟIf you select the wrong dose, you can turn the dose selector clockwise or counterclockwise to the correct dose. See figure L.

The Pen “clicks” sound and feel differently when the dose selector is turned clockwise, counterclockwise, or if you forcefully move it past the number of “mg” left in the Pen.

Step 4. Inject your dose

- Select the injection site.
- Norditropin can be injected under the skin (subcutaneously) of your stomach area (abdomen), buttocks, upper legs (thighs), or upper arms, as instructed by your healthcare provider. Change the injection site every day.
- Wipe the injection site with an alcohol swab and let the area dry.
- Insert the needle into your skin as your healthcare provider has shown you. See figure M.
Make sure you can see the dose counter. Do not cover it with your fingers. This could block the injection.

- Press and hold down the dose button until the dose counter shows “0”. See figure N. The “0” must line up with the dose pointer. You may then hear or feel a “click”.
- Continue to hold the needle in your skin.

ꜟIf “0” does not appear in the dose counter after continuously pressing the dose button, your needle may be blocked or damaged, see Frequently Asked Questions.

- Keep the needle in your skin after the dose counter has returned to “0”. Count slowly to 6 to ensure that the full dose has been delivered. See figure O.

- Carefully remove the needle from your skin. See figure P. If blood appears at the injection site, press lightly with a gauze pad. Do not rub the area.

ꜟYou may see a drop of Norditropin at the needle tip after injecting. This is normal and does not affect your dose.

Step 5. After your injection

- Carefully remove the needle from the Pen by turning the needle counterclockwise. See figure Q.

- Place the needle in a sharps disposal container immediately to reduce the risk of a needle stick. See figure R.

ꜟAlways dispose of the needle after each injection.

For further information about safe sharps disposal, see Frequently Asked Questions.

ꜟDo not try to put the needle cap back on. You may stick yourself with the needle.

- Put the Pen cap on your Pen after each use to protect the Norditropin from direct light. See figure S.
See “How should I store Norditropin?”

- Always remove the needle from your Pen. This reduces the risk of contamination, infection, leakage of Norditropin, and blocked needles leading to incorrect dosing.

How should I store Norditropin?

- Before you use Norditropin FlexPro pens for the first time:
- Store your new, unused Norditropin pen in a refrigerator between 36ºF to 46ºF (2ºC to 8ºC).
- Do not freeze Norditropin.
- When stored in the refrigerator, do not store Norditropin directly next to the cooling element.
- Keep Norditropin away from direct light.
- Do not use Norditropin that has been frozen or in temperatures warmer than 77ºF (25ºC).
- Do not use Norditropin after the expiration date printed on the carton and the pen.
- After you use Norditropin FlexPro pens and there is still medicine left:
- Store remaining Norditropin in the refrigerator between 36ºF to 46ºF (2ºC to 8ºC) and use within 4 weeks, or
- Store remaining Norditropin at room temperature no warmer than 77ºF (25ºC) and use within 3
weeks.
Keep Norditropin and all medicines out of the reach of children.

Frequently Asked Questions

How do I see how

much Norditropin is

left in my Pen?

The Pen scale shows you approximately how much Norditropin is left in your Pen. See figure T.

To see how much Norditropin is left in your Pen, use the dose counter: Turn the dose selector clockwise until the dose counter stops. The dose pointer will line up with the number of “mg” left in the Pen. You can select a maximum dose of 2.0 mg. If the dose counter stops with the dose pointer lined up with “2.0”, at least 2.0 mg are left in your Pen.

If the dose counter stops with the dose pointer lined up with “1.25”, only 1.25 mg are left in your Pen. See figure U.

What if I need a larger dose than what is left in my Pen?

It is not possible to select a larger dose on the dose counter than the number of “mg” left in your Pen.

If you need more Norditropin than you have left in your Pen, you can use a new Pen or split your dose between your current Pen and a new Pen. Only split your dose if you have been trained or advised by your healthcare provider on how to do this. You may find it helpful to use a calculator to plan the doses as instructed by your healthcare provider.

Be very careful to calculate your split dose correctly so that you do not give the wrong dose. If you are not sure how to split your dose using two Pens, then select and inject the dose you need with a new Pen.

What if no Norditropin appears when I check the flow?

A. Your needle may be blocked or damaged, if no Norditropin appears at the needle tip. Remove the needle as described in step 5 and repeat steps 1 and 2.

B. Your Pen may be defective, if Norditropin still does not appear after changing the needle. Do not use the Pen. Contact Novo Nordisk at 1-888-668-6444.

What if “0” does not appear after completing my injection?

The needle may be blocked or damaged, and you have not received any Norditropin – even though the dose counter has moved from the dose that you have set. Remove the needle as described in step 5 and repeat steps 1 to 4.

If “0” still does not appear after completing the injection, contact Novo Nordisk at 1-888-668-6444.

How should I take care of my Pen?

Be careful not to drop your Pen or knock it against hard surfaces. Do not expose your Pen to dust, dirt, liquid, or direct light.

See “How should I store Norditropin?”.

Do not try to refill your Pen, it is already prefilled. When your Pen is empty, throw it away and use a new pen. See “How do I dispose of used needles and Pens?”.

Frequently Asked Questions

What if I drop my Pen?

If you drop your Pen or think that something is wrong with it, attach a new disposable needle and check the Norditropin flow before you inject, see steps 1 and 2. Do not try to repair your Pen or pull it apart.

How do I clean my Pen?

Do not wash, soak, or lubricate your Pen. If necessary, clean it with mild detergent on a moistened cloth.

How do I dispose of used needles and Pens?

Put your used needles in an FDA-cleared sharps disposal container right away after use. Do not throw away (dispose of) loose needles in your household trash. If you do not have an FDA-cleared sharps disposal container, you may use a household container that is:

- made of a heavy-duty plastic,
- can be closed with a tight-fitting, puncture-resistant lid, without sharps being able to come out,
- upright and stable during use,
- leak-resistant, and
- properly labeled to warn of hazardous waste inside the container.

When your sharps disposal container is almost full, you will need to follow your community guidelines for the right way to dispose of your sharps disposal container. There may be state or local laws about how you should dispose of used needles and Pens. For more information about safe sharps disposal, and for specific information about safe sharps disposal in the state that you live in, go to the FDA’s website at: http://www.fda.gov/safesharpsdisposal.

Do not dispose of your used sharps disposal container in your household trash unless your community guidelines permit this.

Do not recycle your used sharps disposal container.

When there is not enough medicine left in your Pen for your prescribed dose, the Pen may be thrown away in your household trash after you have removed the needle.

ꜟImportant information

- Caregivers must be very careful when handling needles to reduce the risk of needle sticks and infection.
- Norditropin® FlexPro® 5 mg/1.5 mL Pen is compatible with FlexPro® PenMate®.

www.norditropin.com

This Instructions for Use has been approved by the U.S. Food and Drug Administration.

Norditropin® and FlexPro® are registered trademarks of Novo Nordisk Health Care AG.

Novo Nordisk® and PenMate® are registered trademarks of Novo Nordisk A/S.

PATENT Information: http://novonordisk-us.com/products/product-patents.html

Manufactured by:

Novo Nordisk Inc.

800 Scudders Mill Road

Plainsboro, NJ 08536

U.S. License No. 1261

For information about NORDITROPIN®

Visit: norditropin.com

Or call: 1 (888) 668-6444

Revised: 01/2025

© 2025 Novo Nordisk A/S

Instructions for Use – 10mg

INSTRUCTIONS FOR USE
NORDITROPIN ® [nor-dee-tro-pin]
(somatropin)
injection, for subcutaneous use
10mg

Norditropin FlexPro Pen is for single-patient-use only.

Supplies you will need:

- Norditropin FlexPro prefilled Pen new injection needle. Norditropin prefilled Pen is designed to be used with all Novo Nordisk disposable needles up to a length of 8 mm.
- sharps disposal container. See step 5 for information on how to throw away (dispose of) used needles and Pens.
- alcohol pad
- gauze pad

How to use your Norditropin FlexPro Pen

5 steps you should follow for a Norditropin injection:

Step 1: Prepare your Norditropin FlexPro Pen
Step 2: Check the Norditropin flow with each new Pen
Step 3: Select your dose
Step 4: Inject your dose
Step 5: After your injection

For further information about your Pen see:

Frequently Asked Questions
Important information
Patient Information

ꜝImportant information

Make sure that you read this information carefully.

ꜟAdditional information

Norditropin is for use under the skin only (subcutaneous).

Do not share your Norditropin Pen and needles with another person. You may give another person an infection or get an infection from them.

Do not use your Pen without proper training from your healthcare provider.

Make sure that you are confident in giving an injection with the Pen before you start your treatment.

If you are blind or have poor eyesight and cannot read the dose counter on the Pen, do not use this Pen without help. Get help from a person with good eyesight who is trained to use the Pen.

Step 1. Prepare your Norditropin FlexPro Pen

- Wash your hands with soap and water.
  1. Check the name, strength, and colored label on your Pen to make sure that it contains Norditropin in the right strength.
  1. Pull off the Pen cap.
  1. Turn the Pen upside down 1 or 2 times to check that the Norditropin in your Pen is clear and colorless. See figure A. If the Norditropin looks cloudy, do not use the Pen.

- When you are ready to give your injection, take a new disposable needle, and remove the paper tab.
- Push the needle straight onto the Pen. Turn the needle clockwise until it is on tight. See figure B.

ꜟAlways use a new needle for each injection. This reduces the risk of contamination, infection, leakage of Norditropin, and blocked needles leading to incorrect dosing.

- Pull off the outer needle cap and dispose of it. See figure C.

- Pull off the inner needle cap and dispose of it. See figure D.

ꜟA drop of Norditropin may appear at the needle tip. This is normal, but you must still check the Norditropin flow with each new Pen. See step 2.

ꜝNever use a bent or damaged needle.

Step 2. Check the Norditropin flow with each new Pen

ꜟIf your Pen is already in use, go to step 3.

Before using a new Pen, check the Norditropin flow to make sure the growth hormone can flow through the Pen and needle.

1. Turn the dose selector clockwise 1 tick marking on the dose counter to select 0.05 mg. You will hear a faint “click” when you turn the dose selector. See figure E.

- 1 marking on the dose counter equals 0.05 mg. See figure F.

- Hold the Pen with the needle pointing up. Press and hold in the dose button until the dose counter returns to “0”. The “0” must line up with the dose pointer. See figure G.

- Check that a drop of Norditropin appears at the needle tip. See figure H.

ꜟIf no Norditropin appears, repeat step 2 up to 6 times.

If you still do not see a drop of Norditropin, change the needle:

- Carefully remove the needle from the Pen by turning the needle counterclockwise. Place the needle in a sharps disposal container immediately. See step 5.
- and repeat step 2 again.
Do not use the Pen if a drop of Norditropin still does not appear after changing the needle and repeating step 2. Call Novo Nordisk at
1-888-668-6444 for help.

Step 3. Select your dose

- To start, check that the dose pointer is set at “0”.
- Turn the dose selector clockwise to select the dose you need. See figure I.
When you have selected your dose, you can go to step 4.

ꜟIf there is not enough Norditropin left to select a full dose, see Frequently Asked Questions.

ꜟThe dose counter shows the dose in “mg”. See figures J and K. Always use the dose counter to select the exact dose. Do not use the “click” sounds you hear when you turn the dose selector or the Pen scale to select your dose. Only the dose pointer on the dose counter will show the exact dose selected.

ꜟIf you select the wrong dose, you can turn the dose selector clockwise or counterclockwise to the correct dose. See figure L.

The Pen “clicks” sound and feel differently when the dose selector is turned clockwise, counterclockwise, or if you forcefully move it past the number of “mg” left in the Pen.

Step 4. Inject your dose

- Select the injection site.
  1. Norditropin can be injected under the skin (subcutaneously) of your stomach area (abdomen), buttocks, upper legs (thighs), or upper arms, as instructed by your healthcare provider. Change the injection site every day.
- Wipe the injection site with an alcohol swab and let the area dry.
- Insert the needle into your skin as your healthcare provider has shown you. See figure M.
Make sure you can see the dose counter. Do not cover it with your fingers. This could block the injection.

- Press and hold down the dose button until the dose counter shows “0”. See figure N. The “0” must line up with the dose pointer. You may then hear or feel a “click”.
- Continue to hold the needle in your skin.

ꜟIf “0” does not appear in the dose counter after continuously pressing the dose button, your needle may be blocked or damaged, see Frequently Asked Questions.

- Keep the needle in your skin after the dose counter has returned to “0”. Count slowly to 6 to ensure that the full dose has been delivered. See figure O.

- Carefully remove the needle from your skin. See figure P. If blood appears at the injection site, press lightly with a gauze pad. Do not rub the area.

ꜟYou may see a drop of Norditropin at the needle tip after injecting. This is normal and does not affect your dose.

Step 5. After your injection

- Carefully remove the needle from the Pen by turning the needle counterclockwise. See figure Q.

- Place the needle in a sharps disposal container immediately to reduce the risk of a needle stick. See figure R.

ꜟAlways dispose of the needle after each injection.

For further information about safe sharps disposal, see Frequently Asked Questions.

ꜝDo not try to put the needle cap back on. You may stick yourself with the needle.

- Put the Pen cap on your Pen after each use to protect the Norditropin from direct light. See figure S.
See “How should I store Norditropin?”.

ꜝAlways remove the needle from your Pen. This reduces the risk of contamination, infection, leakage of Norditropin, and blocked needles leading to incorrect dosing.

How should I store Norditropin?

•Before you use Norditropin FlexPro pens for the first time:

- Store your new, unused Norditropin pen in a refrigerator between 36ºF to 46ºF (2ºC to 8ºC).
- Do not freeze Norditropin.
- When stored in the refrigerator, do not store Norditropin directly next to the cooling element.
- Keep Norditropin away from direct light.
- Do not use Norditropin that has been frozen or in temperatures warmer than 77ºF (25ºC).
- Do not use Norditropin after the expiration date printed on the carton and the pen.

•After you use Norditropin FlexPro pens and there is still medicine left:

- Store remaining Norditropin in the refrigerator between 36ºF to 46ºF (2ºC to 8ºC) and use within 4 weeks, or
- Store remaining Norditropin at room temperature no warmer than 77ºF (25ºC) and use within 3 weeks.

Keep Norditropin and all medicines out of the reach of children.

Frequently Asked Questions

How do I see how

much Norditropin is

left in my Pen?

The Pen scale shows you approximately how much Norditropin is left in your Pen. See figure T.

To see how much Norditropin is left in your Pen, use the dose counter: Turn the dose selector clockwise until the dose counter stops. The dose pointer will line up with the number of “mg” left in the Pen. You can select a maximum dose of 4.0 mg. If the dose counter stops with the dose pointer lined up with “4.0”, at least 4.0 mg are left in your Pen.

If the dose counter stops with the dose pointer lined up with “2.4”, only 2.4 mg are left in your Pen. See figure U.

What if I need a larger dose than what is left in my Pen?

It is not possible to select a larger dose on the dose counter than the number of “mg” left in your Pen.

If you need more Norditropin than you have left in your Pen, you can use a new Pen or split your dose between your current Pen and a new Pen. Only split your dose if you have been trained or advised by your healthcare provider on how to do this. You may find it helpful to use a calculator to plan the doses as instructed by your healthcare provider.

Be very careful to calculate your split dose correctly so that you do not give the wrong dose. If you are not sure how to split your dose using two Pens, then select and inject the dose you need with a new Pen.

What if no Norditropin appears when I check the flow?

A. Your needle may be blocked or damaged, if no Norditropin appears at the needle tip. Remove the needle as described in step 5 and repeat steps 1 and 2.

B. Your Pen may be defective, if Norditropin still does not appear after changing the needle. Do not use the Pen. Contact Novo Nordisk at 1-888-668-6444.

What if “0” does not appear after completing my injection?

The needle may be blocked or damaged, and you have not received any Norditropin – even though the dose counter has moved from the dose that you have set. Remove the needle as described in step 5 and repeat steps 1 to 4.

If “0” still does not appear after completing the injection, contact Novo Nordisk at 1-888-668-6444.

How should I take care of my Pen?

Be careful not to drop your Pen or knock it against hard surfaces. Do not expose your Pen to dust, dirt, liquid, or direct light.

See “How should I store Norditropin?”.

Do not try to refill your Pen, it is already prefilled. When your Pen is empty, throw it away and use a new pen. See “How do I dispose of used needles and Pens?”.

Frequently Asked Questions

What if I drop my Pen?

If you drop your Pen or think that something is wrong with it, attach a new disposable needle and check the Norditropin flow before you inject, see steps 1 and 2. Do not try to repair your Pen or pull it apart.

How do I clean my Pen?

Do not wash, soak, or lubricate your Pen. If necessary, clean it with mild detergent on a moistened cloth.

How do I dispose of used needles and Pens?

Put your used needles in an FDA-cleared sharps disposal container right away after use. Do not throw away (dispose of) loose needles in your household trash. If you do not have an FDA-cleared sharps disposal container, you may use a household container that is:

• made of a heavy-duty plastic,
• can be closed with a tight-fitting, puncture-resistant lid, without sharps being able to come out,
• upright and stable during use,
• leak-resistant, and
• properly labeled to warn of hazardous waste inside the container.

When your sharps disposal container is almost full, you will need to follow your community guidelines for the right way to dispose of your sharps disposal container. There may be state or local laws about how you should dispose of used needles and Pens. For more information about safe sharps disposal, and for specific information about safe sharps disposal in the state that you live in, go to the FDA’s website at: http://www.fda.gov/safesharpsdisposal.

Do not dispose of your used sharps disposal container in your household trash unless your community guidelines permit this.

Do not recycle your used sharps disposal container.

When there is not enough medicine left in your Pen for your prescribed dose, the Pen may be thrown away in your household trash after you have removed the needle.

ꜝImportant information

- Caregivers must be very careful when handling needles to reduce the risk of needle sticks and infection.
- Norditropin® FlexPro® 10 mg/1.5 mL Pen is compatible with FlexPro® PenMate®.

www.norditropin.com

This Instructions for Use has been approved by the U.S. Food and Drug Administration.

Norditropin® and FlexPro® are registered trademarks of Novo Nordisk Health Care AG.

Novo Nordisk® and PenMate® are registered trademarks of Novo Nordisk A/S.

PATENT Information: http://novonordisk-us.com/products/product-patents.html

Manufactured by:

Novo Nordisk Inc.

800 Scudders Mill Road

Plainsboro, NJ 08536 USA

U.S. License No. 1261

For information about NORDITROPIN®

Visit: norditropin.com

Or call: 1 (888) 668-6444

Revised: 01/2025

© 2025 Novo Nordisk A/S

Instructions for Use – 15mg

INSTRUCTIONS FOR USE
NORDITROPIN® [nor-dee-tro-pin]
(somatropin)
injection, for subcutaneous use
15mg

Norditropin FlexPro Pen is for single-patient-use only.

Supplies you will need:

- Norditropin FlexPro prefilled Pen new injection needle. Norditropin prefilled Pen is designed to be used with all Novo Nordisk disposable needles up to a length of 8 mm
- sharps disposal container. See step 5 for information on how to throw away (dispose of) used needles and Pens.
- alcohol pad
- gauze pad

How to use your Norditropin FlexPro Pen

5 steps you should follow for a Norditropin injection:

Step 1: Prepare your Norditropin FlexPro Pen
Step 2: Check the Norditropin flow with each new Pen
Step 3: Select your dose
Step 4: Inject your dose
Step 5: After your injection

For further information about your Pen see:

Frequently Asked Questions
Important information
Patient Information

ꜝImportant information

Make sure that you read this information carefully.

ꜟAdditional information

Norditropin is for use under the skin only (subcutaneous).

Do not share your Norditropin Pen and needles with another person. You may give another person an infection or get an infection from them.

Do not use your Pen without proper training from your healthcare provider.

Make sure that you are confident in giving an injection with the Pen before you start your treatment.

If you are blind or have poor eyesight and cannot read the dose counter on the Pen, do not use this Pen without help. Get help from a person with good eyesight who is trained to use the Pen.

Step 1. Prepare your Norditropin FlexPro Pen

- Wash your hands with soap and water.
- Check the name, strength, and colored label on your Pen to make sure that it contains Norditropin in the right strength.
- Pull off the Pen cap.
- Turn the Pen upside down 1 or 2 times to check that the Norditropin in your Pen is clear and colorless.
- See figure A. If the Norditropin looks cloudy, do not use the Pen.

- When you are ready to give your injection, take a new disposable needle, and remove the paper tab.
- Push the needle straight onto the Pen. Turn the needle clockwise until it is on tight. See figure B.

ꜝAlways use a new needle for each injection. This reduces the risk of contamination, infection, leakage of Norditropin, and blocked needles leading to incorrect dosing.

- Pull off the outer needle cap and dispose of it. See figure C.

- Pull off the inner needle cap and dispose of it. See figure D.

ꜟA drop of Norditropin may appear at the needle tip. This is normal, but you must still check the Norditropin flow with each new Pen. See step 2.

ꜝNever use a bent or damaged needle.

Step 2. Check the Norditropin flow with each new Pen

ꜟIf your Pen is already in use, go to step 3.

Before using a new Pen, check the Norditropin flow to make sure the growth hormone can flow through the Pen and needle.

1. Turn the dose selector clockwise 1 tick marking on the dose counter to select 0.1 mg. You will hear a faint “click” when you turn the dose selector. See figure E.

- 1 marking on the dose counter equals 0.1 mg. See figure F.

- Hold the Pen with the needle pointing up. Press and hold in the dose button until the dose counter returns to “0”. The “0” must line up with the dose pointer. See figure G.

- Check that a drop of Norditropin appears at the needle tip. See figure H.

ꜟIf no Norditropin appears, repeat step 2 up to 6 times.

If you still do not see a drop of Norditropin, change the needle:

- Carefully remove the needle from the Pen by turning the needle counterclockwise. Place the needle in a sharps disposal container immediately. See step 5.
- and repeat step 2 again.
Do not use the Pen if a drop of Norditropin still does not appear after changing the needle and repeating step 2. Call Novo Nordisk at
1-888-668-6444 for help.

Step 3. Select your dose

- To start, check that the dose pointer is set at “0”.
- Turn the dose selector clockwise to select the dose you need. See figure I.
When you have selected your dose, you can go to step 4.

ꜟIf there is not enough Norditropin left to select a full dose, see Frequently Asked Questions.

ꜟThe dose counter shows the dose in “mg”. See figures J and K. Always use the dose counter to select the exact dose. Do not use the “click” sounds you hear when you turn the dose selector or the Pen scale to select your dose.Only the dose pointer on the dose counter will show the exact dose selected.

ꜟIf you select the wrong dose, you can turn the dose selector clockwise or counterclockwise to the correct dose. See figure L.

The Pen “clicks” sound and feel differently when the dose selector is turned clockwise, counterclockwise, or if you forcefully move it past the number of “mg” left in the Pen.

Step 4. Inject your dose

- Select the injection site.
- Norditropin can be injected under the skin (subcutaneously) of your stomach area (abdomen), buttocks, upper legs (thighs), or upper arms, as instructed by your healthcare provider. Change the injection site every day.
- Wipe the injection site with an alcohol swab and let the area dry.
- Insert the needle into your skin as your healthcare provider has shown you. See figure M.
Make sure you can see the dose counter. Do not cover it with your fingers. This could block the injection.

- Press and hold down the dose button until the dose counter shows “0”. See figure N. The “0” must line up with the dose pointer. You may then hear or feel a “click”.
- Continue to hold the needle in your skin.

ꜟIf “0” does not appear in the dose counter after continuously pressing the dose button, your needle may be blocked or damaged, see Frequently Asked Questions.

- Keep the needle in your skin after the dose counter has returned to “0”. Count slowly to 6 to ensure that the full dose has been delivered. See figure O.

- Carefully remove the needle from your skin. See figure P. If blood appears at the injection site, press lightly with a gauze pad. Do not rub the area.

ꜟYou may see a drop of Norditropin at the needle tip after injecting. This is normal and does not affect your dose.

Step 5. After your injection

- Carefully remove the needle from the Pen by turning the needle counterclockwise. See figure Q.

- Place the needle in a sharps disposal container immediately to reduce the risk of a needle stick. See figure R.

ꜟAlways dispose of the needle after each injection.

For further information about safe sharps disposal, see Frequently Asked Questions.

ꜝDo not try to put the needle cap back on. You may stick yourself with the needle.

- Put the Pen cap on your Pen after each use to protect the Norditropin from direct light. See figure S.
See “How should I store Norditropin?”.

ꜝAlways remove the needle from your Pen. This reduces the risk of contamination, infection, leakage of Norditropin, and blocked needles leading to incorrect dosing.

How should I store Norditropin?

•Before you use Norditropin FlexPro pens for the first time:

- Store your new, unused Norditropin pen in a refrigerator between 36ºF to 46ºF (2ºC to 8ºC).
- Do not freeze Norditropin.
- When stored in the refrigerator, do not store Norditropin directly next to the cooling element.
- Keep Norditropin away from direct light.
- Do not use Norditropin that has been frozen or in temperatures warmer than 77ºF (25ºC).
- Do not use Norditropin after the expiration date printed on the carton and the pen.
•After you use Norditropin FlexPro pens and there is still medicine left:
- Store remaining Norditropin in the refrigerator between 36ºF to 46ºF (2ºC to 8ºC) and use within 4 weeks, or
- Store remaining Norditropin at room temperature no warmer than 77ºF (25ºC) and use within 3 weeks.

Keep Norditropin and all medicines out of the reach of children.

Frequently Asked Questions

How do I see how

much Norditropin is

left in my Pen?

The Pen scale shows you approximately how much Norditropin is left in your Pen. See figure T.

To see how much Norditropin is left in your Pen, use the dose counter: Turn the dose selector clockwise until the dose counter stops. The dose pointer will line up with the number of “mg” left in the Pen. You can select a maximum dose of 8.0 mg. If the dose counter stops with the dose pointer lined up with “8.0”, at least 8.0 mg are left in your Pen.

If the dose counter stops with the dose pointer lined up with “3.8”, only 3.8 mg are left in your Pen. See figure U.

What if I need a larger dose than what is left in my Pen?

It is not possible to select a larger dose on the dose counter than the number of “mg” left in your Pen.

If you need more Norditropin than you have left in your Pen, you can use a new Pen or split your dose between your current Pen and a new Pen. Only split your dose if you have been trained or advised by your healthcare provider on how to do this. You may find it helpful to use a calculator to plan the doses as instructed by your healthcare provider.

Be very careful to calculate your split dose correctly so that you do not give the wrong dose. If you are not sure how to split your dose using two Pens, then select and inject the dose you need with a new Pen.

What if no Norditropin appears when I check the flow?

A. Your needle may be blocked or damaged, if no Norditropin appears at the needle tip. Remove the needle as described in step 5 and repeat steps 1 and 2.

B. Your Pen may be defective, if Norditropin still does not appear after changing the needle. Do not use the Pen. Contact Novo Nordisk at 1-888-668-6444.

What if “0” does not appear after completing my injection?

The needle may be blocked or damaged, and you have not received any Norditropin – even though the dose counter has moved from the dose that you have set. Remove the needle as described in step 5 and repeat steps 1 to 4.

If “0” still does not appear after completing the injection, contact Novo Nordisk at 1-888-668-6444.

How should I take care of my Pen?

Be careful not to drop your Pen or knock it against hard surfaces. Do not expose your Pen to dust, dirt, liquid, or direct light.

See “How should I store Norditropin?”.

Do not try to refill your Pen, it is already prefilled. When your Pen is empty, throw it away and use a new pen. See “How do I dispose of used needles and Pens?”.

Frequently Asked Questions

What if I drop my Pen?

If you drop your Pen or think that something is wrong with it, attach a new disposable needle and check the Norditropin flow before you inject, see steps 1 and 2. Do not try to repair your Pen or pull it apart.

How do I clean my Pen?

Do not wash, soak, or lubricate your Pen. If necessary, clean it with mild detergent on a moistened cloth.

How do I dispose of used needles and Pens?

Put your used needles in an FDA-cleared sharps disposal container right away after use. Do not throw away (dispose of) loose needles in your household trash. If you do not have an FDA-cleared sharps disposal container, you may use a household container that is:

• made of a heavy-duty plastic,
• can be closed with a tight-fitting, puncture-resistant lid, without sharps being able to come out,
• upright and stable during use,
• leak-resistant, and
• properly labeled to warn of hazardous waste inside the container.

When your sharps disposal container is almost full, you will need to follow your community guidelines for the right way to dispose of your sharps disposal container. There may be state or local laws about how you should dispose of used needles and Pens. For more information about safe sharps disposal, and for specific information about safe sharps disposal in the state that you live in, go to the FDA’s website at: http://www.fda.gov/safesharpsdisposal.

Do not dispose of your used sharps disposal container in your household trash unless your community guidelines permit this.

Do not recycle your used sharps disposal container.

When there is not enough medicine left in your Pen for your prescribed dose, the Pen may be thrown away in your household trash after you have removed the needle.

ꜟImportant information

- Caregivers must be very careful when handling needles to reduce the risk of needle sticks and infection.
- Norditropin® FlexPro® 15 mg/1.5 mL Pen is compatible with FlexPro® PenMate®.

www.norditropin.com

This Instructions for Use has been approved by the U.S. Food and Drug Administration.

Norditropin® and FlexPro® are registered trademarks of Novo Nordisk Health Care AG.

Novo Nordisk® and PenMate® are registered trademarks of Novo Nordisk A/S.

PATENT Information: http://novonordisk-us.com/products/product-patents.html

Manufactured by:

Novo Nordisk Inc.

800 Scudders Mill Road

Plainsboro, NJ 08536

U.S. License No. 1261

For information about NORDITROPIN®

Visit: norditropin.com

Or call: 1 (888) 668-6444

Revised: 01/2025

© 2025 Novo Nordisk A/S

Instructions for Use – 30mg

INSTRUCTIONS FOR USE

NORDITROPIN®[nor-dee-tro-pin]
(somatropin)
injection, for subcutaneous use
30mg

Norditropin FlexPro Pen is for single-patient-use only.

Supplies you will need:

- Norditropin FlexPro prefilled Pen new injection needle. Norditropin prefilled Pen is designed to be used with all Novo Nordisk disposable needles up to a length of 8 mm
- sharps disposal container. See step 5 for information on how to throw away (dispose of) used needles and Pens.
- alcohol pad
- gauze pad

How to use your Norditropin FlexPro Pen

5 steps you should follow for a Norditropin injection:

Step 1: Prepare your Norditropin FlexPro Pen
Step 2: Check the Norditropin flow with each new Pen
Step 3: Select your dose
Step 4: Inject your dose
Step 5: After your injection

For further information about your Pen see:

Frequently Asked Questions
Important information
Patient Information

ꜝImportant information

Make sure that you read this information carefully.

ꜟAdditional information

Norditropin is for use under the skin only (subcutaneous).

Do not share your Norditropin Pen and needles with another person. You may give another person an infection or get an infection from them.

Do not use your Pen without proper training from your healthcare provider.

Make sure that you are confident in giving an injection with the Pen before you start your treatment.

If you are blind or have poor eyesight and cannot read the dose counter on the Pen, do not use this Pen without help. Get help from a person with good eyesight who is trained to use the Pen.

Step 1. Prepare your Norditropin FlexPro Pen

- Wash your hands with soap and water.
- Check the name, strength, and colored label on your Pen to make sure that it contains Norditropin in the right strength.
- Pull off the Pen cap.
- Turn the Pen upside down 1 or 2 times to check that the Norditropin in your Pen is clear and colorless.
See figure A. If the Norditropin looks cloudy, do not use the Pen.

- When you are ready to give your injection, take a new disposable needle, and remove the paper tab.
- Push the needle straight onto the Pen. Turn the needle clockwise until it is on tight. See figure B.

ꜝAlways use a new needle for each injection. This reduces the risk of contamination, infection, leakage of Norditropin, and blocked needles leading to incorrect dosing.

- Pull off the outer needle cap and dispose of it. See figure C.

- Pull off the inner needle cap and dispose of it. See figure D.

ꜟA drop of Norditropin may appear at the needle tip. This is normal, but you must still check the Norditropin flow with each new Pen. See step 2.

ꜝNever use a bent or damaged needle.

Step 2. Check the Norditropin flow with each new Pen

ꜟIf your Pen is already in use, go to step 3.

Before using a new Pen, check the Norditropin flow to make sure the growth hormone can flow through the Pen and needle.

1. Turn the dose selector clockwise 1 tick marking on the dose counter to select 0.1 mg. You will hear a faint “click” when you turn the dose selector. See figure E.

- 1 marking on the dose counter equals 0.1 mg. See figure F.

- Hold the Pen with the needle pointing up. Press and hold in the dose button until the dose counter returns to “0”. The “0” must line up with the dose pointer. See figure G.

- Check that a drop of Norditropin appears at the needle tip. See figure H.

ꜟIf no Norditropin appears, repeat step 2 up to 6 times.

If you still do not see a drop of Norditropin, change the needle:

- Carefully remove the needle from the Pen by turning the needle counterclockwise. Place the needle in a sharps disposal container immediately. See step 5.
- and repeat step 2 again.
Do not use the Pen if a drop of Norditropin still does not appear after changing the needle and repeating step 2. Call Novo Nordisk at
1-888-668-6444 for help.

Step 3. Select your dose

- To start, check that the dose pointer is set at “0”.
- Turn the dose selector clockwise to select the dose you need. See figure I.
When you have selected your dose, you can go to step 4.

ꜟIf there is not enough Norditropin left to select a full dose, see Frequently Asked Questions.

ꜟThe dose counter shows the dose in “mg”. See figures J and K. Always use the dose counter to select the exact dose. Do not use the “click” sounds you hear when you turn the dose selector or the Pen scale to select your dose. Only the dose pointer on the dose counter will show the exact dose selected.

ꜟIf you select the wrong dose, you can turn the dose selector clockwise or counterclockwise to the correct dose. See figure L.

The Pen “clicks” sound and feel differently when the dose selector is turned clockwise, counterclockwise, or if you forcefully move it past the number of “mg” left in the Pen.

Step 4. Inject your dose

- Select the injection site.
- Norditropin can be injected under the skin (subcutaneously) of your stomach area (abdomen), buttocks, upper legs (thighs), or upper arms, as instructed by your healthcare provider. Change the injection site every day.
- Wipe the injection site with an alcohol swab and let the area dry.
- Insert the needle into your skin as your healthcare provider has shown you. See figure M.
Make sure you can see the dose counter. Do not cover it with your fingers. This could block the injection.

- Press and hold down the dose button until the dose counter shows “0”. See figure N. The “0” must line up with the dose pointer. You may then hear or feel a “click”.
- Continue to hold the needle in your skin.

ꜟIf “0” does not appear in the dose counter after continuously pressing the dose button, your needle may be blocked or damaged, see Frequently Asked Questions.

- Keep the needle in your skin after the dose counter has returned to “0”. Count slowly to 6 to ensure that the full dose has been delivered. See figure O.

- Carefully remove the needle from your skin. See figure P. If blood appears at the injection site, press lightly with a gauze pad. Do not rub the area.

ꜟYou may see a drop of Norditropin at the needle tip after injecting. This is normal and does not affect your dose.

Step 5. After your injection

- Carefully remove the needle from the Pen by turning the needle counterclockwise. See figure Q.

- Place the needle in a sharps disposal container immediately to reduce the risk of a needle stick. See figure R.

ꜟAlways dispose of the needle after each injection.

For further information about safe sharps disposal, see Frequently Asked Questions.

ꜝDo not try to put the needle cap back on. You may stick yourself with the needle.

- Put the Pen cap on your Pen after each use to protect the Norditropin from direct light. See figure S.
See “How should I store Norditropin?”.

ꜟAlways remove the needle from your Pen. This reduces the risk of contamination, infection, leakage of Norditropin, and blocked needles leading to incorrect dosing.

How should I store Norditropin?
•Before you use Norditropin FlexPro pens for the first time:

1. Store your new, unused Norditropin pen in a refrigerator between 36ºF to 46ºF (2ºC to 8ºC).
2. Do not freeze Norditropin.
3. When stored in the refrigerator, do not store Norditropin directly next to the cooling element.
4. Keep Norditropin away from direct light.
5. Do not use Norditropin that has been frozen or in temperatures warmer than 77ºF (25ºC).
6. Do not use Norditropin after the expiration date printed on the carton and the pen.
•After you use Norditropin FlexPro pens and there is still medicine left:
7. Store remaining Norditropin in the refrigerator between 36ºF to 46ºF (2ºC to 8ºC) and use within 4 weeks, or
8. Store remaining Norditropin at room temperature no warmer than 77ºF (25ºC) and use within 3 weeks.
Keep Norditropin and all medicines out of the reach of children.

Frequently Asked Questions

How do I see how

much Norditropin is

left in my Pen?

The Pen scale shows you approximately how much Norditropin is left in your Pen. See figure T.

To see how much Norditropin is left in your Pen, use the dose counter: Turn the dose selector clockwise until the dose counter stops. The dose pointer will line up with the number of “mg” left in the Pen. You can select a maximum dose of 8.0 mg. If the dose counter stops with the dose pointer lined up with “8.0”, at least 8.0 mg are left in your Pen.

If the dose counter stops with the dose pointer lined up with “3.8”, only 3.8 mg are left in your Pen. See figure U.

What if I need a larger dose than what is left in my Pen?

It is not possible to select a larger dose on the dose counter than the number of “mg” left in your Pen.

If you need more Norditropin than you have left in your Pen, you can use a new Pen or split your dose between your current Pen and a new Pen. Only split your dose if you have been trained or advised by your healthcare provider on how to do this. You may find it helpful to use a calculator to plan the doses as instructed by your healthcare provider.

Be very careful to calculate your split dose correctly so that you do not give the wrong dose. If you are not sure how to split your dose using two Pens, then select and inject the dose you need with a new Pen.

What if no Norditropin appears when I check the flow?

A. Your needle may be blocked or damaged, if no Norditropin appears at the needle tip. Remove the needle as described in step 5 and repeat steps 1 and 2.

B. Your Pen may be defective, if Norditropin still does not appear after changing the needle. Do not use the Pen. Contact Novo Nordisk at 1-888-668-6444.

What if “0” does not appear after completing my injection?

The needle may be blocked or damaged, and you have not received any Norditropin – even though the dose counter has moved from the dose that you have set. Remove the needle as described in step 5 and repeat steps 1 to 4.

If “0” still does not appear after completing the injection, contact Novo Nordisk at 1-888-668-6444.

How should I take care of my Pen?

Be careful not to drop your Pen or knock it against hard surfaces. Do not expose your Pen to dust, dirt, liquid, or direct light.

See “How should I store Norditropin?”.

Do not try to refill your Pen, it is already prefilled. When your Pen is empty, throw it away and use a new pen. See “How do I dispose of used needles and Pens?”.

Frequently Asked Questions

What if I drop my Pen?

If you drop your Pen or think that something is wrong with it, attach a new disposable needle and check the Norditropin flow before you inject, see steps 1 and 2. Do not try to repair your Pen or pull it apart.

How do I clean my Pen?

Do not wash, soak, or lubricate your Pen. If necessary, clean it with mild detergent on a moistened cloth.

How do I dispose of used needles and Pens?

Put your used needles in an FDA-cleared sharps disposal container right away after use. Do not throw away (dispose of) loose needles in your household trash. If you do not have an FDA-cleared sharps disposal container, you may use a household container that is:

• made of a heavy-duty plastic,
• can be closed with a tight-fitting, puncture-resistant lid, without sharps being able to come out,
• upright and stable during use,
• leak-resistant, and
• properly labeled to warn of hazardous waste inside the container.

When your sharps disposal container is almost full, you will need to follow your community guidelines for the right way to dispose of your sharps disposal container. There may be state or local laws about how you should dispose of used needles and Pens. For more information about safe sharps disposal, and for specific information about safe sharps disposal in the state that you live in, go to the FDA’s website at: http://www.fda.gov/safesharpsdisposal.

Do not dispose of your used sharps disposal container in your household trash unless your community guidelines permit this.

Do not recycle your used sharps disposal container.

When there is not enough medicine left in your Pen for your prescribed dose, the Pen may be thrown away in your household trash after you have removed the needle.

ꜟImportant information

- Caregivers must be very careful when handling needles to reduce the risk of needle sticks and infection.
- Norditropin® FlexPro® 30 mg/3 mL Pen is not compatible with FlexPro® PenMate®.

www.norditropin.com

This Instructions for Use has been approved by the U.S. Food and Drug Administration.

Norditropin® and FlexPro® are registered trademarks of Novo Nordisk Health Care AG.

Novo Nordisk® and PenMate® are registered trademarks of Novo Nordisk A/S.

PATENT Information: http://novonordisk-us.com/products/product-patents.html

Manufactured by:

Novo Nordisk Inc.

800 Scudders Mill Road

Plainsboro, NJ 08536

U.S. License No. 1261

For information about NORDITROPIN®

Visit: norditropin.com

Or call: 1 (888) 668-6444

Revised: 01/2025

© 2025 Novo Nordisk A/S

Instructions for Use - PenMate

INSTRUCTIONS FOR USE

Norditropin® (nor-dee-tro-pin) FlexPro®

(somatropin)

injection

prefilled pen with PenMate®

and

Sogroya® (suh-GROY-uh)

(somapacitan-beco)

injection

prefilled pen with PenMate®

Read this Instructions for Use before you start using your Pen with PenMate.

- PenMate hides the needle when you inject your Norditropin growth hormone with Norditropin FlexPro 5 mg/1.5 mL, 10 mg/1.5 mL, and 15 mg/1.5 mL Pens or Sogroya growth hormone with Sogroya 5 mg/1.5 mL, 10 mg/1.5 mL, and 15 mg/1.5 mL Pens, so that you cannot see the needle.
- Use your PenMate only after you have been trained by a healthcare provider.
- People who are blind or have poor eyesight should only use the PenMate and Pen with help from a person with good eyesight who is trained to use the PenMate and Pen.
- The figures in this Instructions for Use show PenMate being used with a Norditropin FlexPro 5 mg/1.5 mL Pen and a NovoFine needle that is 8 mm long. Even if you are using a Norditropin FlexPro 10 mg/1.5 mL or 15 mg/1.5 mL Pen or a Sogroya 5 mg/1.5 mL, 10 mg/1.5 mL, or 15 mg/1.5 mL Pen or a different needle that is 8 mm long, the instructions are the same.
- Do not share your Norditropin FlexPro or Sogroya Pens and needles with another person. You may give another person an infection or get an infection from them.

Supplies you will need to use your Pen with PenMate:

- 1 PenMate. See Figure A.
- 1 Norditropin FlexPro Pen or Sogroya Pen. See Figure B. PenMate does not work with other injection devices.
- 1 disposable needle up to 8 mm long.See FigureC. Needles are not included with your PenMate or Pen.
- 2 alcohol swabs. See Figure C.
- a sharps disposal container. See Figure C. See “How should I dispose of my Pen and needles” at the end of these instructions for information on how to throw away (dispose of) used Pens and needles.

Pen:

This pen represents Norditropin FlexPro 5 mg/1.5 mL, 10 mg/1.5 mL or 15 mg/1.5 mL Pen and Sogroya 5 mg/1.5 mL, 10 mg/1.5 mL, and 15 mg/1.5 mL Pen

Needle parts and supplies:

Pen case

Step 1: Preparing your PenwithPenMate:

Wash your hands with soap and water and dry them. Check the name and the colored label on your Pen to make sure it contains the growth hormone strength prescribed by your healthcare provider.

Pull off the PenMate cap.

See Figure E.

Pull off the Pen cap and throw it away.
See Figure F.

You will not need the Pen cap with your PenMate.

Look in the Pen window. Check the liquid medicine in your Pen by turning it upside down 1 or 2 times.

See Figure G.

- Norditropin FlexPro Pen: the liquid in the Norditropin FlexPro Pen should be clear and colorless. If the liquid looks cloudy or you see particles, do not use the Norditropin FlexPro Pen.
- Sogroya Pen: the liquid in the Sogroya Pen should be clear to almost clear and colorless to slightly yellow. If the liquid looks cloudy or you see particles, do not use the Sogroya Pen.

Wipe the front stopper on the needle thread of the Pen with an alcohol swab.
See Figure H.

Insert the Pen into the PenMate. Twist the Pen clockwise until you hear or feel a click.
See Figure I.

The Pen is correctly attached in your PenMate when the display window on the Pen lines up with the insertion button on your PenMate.

Step 2. Attaching the needle to your Pen:

- Do not place a needle on your Pen until you are ready to give an injection.
- Always use a new needle for each injection.
- Do not use a bent or damaged needle.

Get a new disposable needle and tear off the paper tab.

See Figure J.

Holding the Pen with 1 hand, firmly press the needle onto the needle thread of the Pen. Screw the needle in a clockwise direction until the needle will not turn anymore.

See Figure K.

Pull off the outer needle cap and save it.

See Figure L.

You will need the outer needle cap after the injection so you can safely remove the needle from the Pen.

Pull off the inner needle cap and throw it away.
See Figure M.

A drop of liquid may appear at the needle tip. This is normal.

Step 3. Priming a new Pen:

Checking the growth hormone flow in the Pen (priming) is not needed for a Pen you have used before.

If the Pen has already been primed, go to Step 4.

Before you use a new Pen you must prepare it for use. Hold the Pen with 1 hand and turn the dose selector clockwise 1 marking to select the minimumdose.

See Figure N.

You may hear or feel a click when you turn the dose selector.

When you turn the dose selector 1 marking, you select the smallest amount of

medicine for a dose.

See Figure O.

This lowest dose will be used for your Norditropin or Sogroya flow check dose.

Hold your Pen with PenMate with the needle pointing up. You may see air bubbles in the PenMate window. Gently tap the top of PenMate a few times to let any air bubbles rise to the top.

See Figure P.

Press the dose button until the dose pointer lines up with the “0” in the display window on the Pen and a drop of liquid appears at the needle tip.

See Figure Q.

If no drop of liquid appears at the needle tip, repeat Step 3 again up to 6 times.

If there is still no drop of liquid at the needle tip, change the needle and repeat Step 3 again.

If a drop of liquid still does not appear at the needle tip after repeating Step 3 and changing the needle, call Novo Nordisk at 1-888-668-6444 for help.

Step 4. Selecting the correct dose of Norditropin or Sogroya:

Use the dose selector on your Pen to make sure you have the exact dose selected. Your dose will be in a certain number of mg (milligrams).

To start, check that the dose pointer on the Pen is set at “0”.

Select the dose you need by turning the dose selector clockwise. If you move past your dose, turn the dose selector counterclockwise until the right number of mg lines up with the dose pointer. See Figure R.

To guide you, the dose selector click sound is different when turned clockwise (softer click) or counterclockwise (louder click). You will hear a click for every single unit dialed.

When dialing counterclockwise, be careful not to press the dose button as liquid will come out.

You can use the growth hormone scale on the side of the Pen to see about how much growth hormone is left in the Pen. You can also use the dose selector to see exactly how much growth hormone is left in the Pen.

If the Pen contains less than 2 mg, 4 mg, or 8 mg (depending on whether you use a 5 mg/1.5 mL, 10 mg/1.5 mL, or 15 mg/1.5 mL Pen), turn the dose selector until it stops. The number that lines up with the dose pointer shows how many mg are left in the Pen. You cannot set a dose higher than the number of mg left in the Pen.

If there is not enough Norditropin or Sogroya left in the Pen for your full dose, use a new Norditropin FlexPro Pen or Sogroya Pen to inject the remaining amount of your dose or contact your healthcare provider.

Remember to subtract the dose already received. For example, if the dose is 0.7 mg and you can only set the dose selector to 0.35 mg, you should inject another 0.35 mg with a new Norditropin FlexPro Pen or Sogroya Pen.

Important:

- Do not use the Pen clicks to count the number of mg you select. Only the display window and dose pointer will show the exact number.
- Do not use the growth hormone scale to measure how much liquid to inject. Only the display window and dose pointer will show the exact number.

Step 5. Selecting your injection site and injecting the dose of Norditropin or Sogroya:

Change your injection site every day. Select the injection site and wipe your skin with an alcohol swab as your healthcare provider showed you.

Norditropin or Sogroya can be injected under your skin (subcutaneously) of your buttocks, stomach area (abdomen), upper legs (thighs), upper arms, or as instructed by your healthcare provider.

See Figure S.

Hold onto both the PenMate and your Pen without touching the insertion button on the PenMate or the dose button on the Pen.

Do not press the insertion button on the PenMate before you are ready to inject your dose. This lowers the risk of hurting yourself with the needle.

Hold the PenMate firmly with 1 hand and pull the Pen out with your other hand until you hear and feel a click. See Figure T.

The needle is now hidden in PenMate.

Norditropin and Sogroya is for use under your skin only (subcutaneous). Hold the PenMate against your skin. Press the insertion button on the PenMate until you hear or feel a click.

When you hear or feel the click, the needle has been inserted automatically into your skin.

See Figure U.

You are now ready to inject your dose.

Press the dose button on the Pen to inject your dose.Do not turn the dose button while you are pressing it. If you turn the dose button, you will not inject growth hormone.

Make sure you can see the display window. Do not cover it with your fingers.

Press and hold down the dose button on the Pen until the display window returns to “0”.

The “0” must line up with the dose pointer. You may then hear or feel a firm click.

After the display window has returned to “0”, leave the needle under your skin for at least 6 seconds to make sure you get your full dose.

See Figure V.

Let go of the dose button while you wait.

See Figure V.

If the dose button cannot be pushed in completely or “0” does not appear in the display window, you did not receive the full dose. Call Novo Nordisk at 1-888-668-6444 for help. You may need a new Pen.

Important:

Always press the dose button to inject the dose. Turning the dose selector will not inject the dose.

Do not touch the display window when you inject, as this can block the injection.

Carefully lift the Pen to remove the needle from the skin.

See Figure W.

Step 6. What to do after your injection is completed:

Carefully put the outer needle cap back on the needle.

Remove the needle from the Pen after each injection.

See Figure X.

Unscrew the needle by turning it counterclockwise. Do not touch the needle. Hold the Pen with 1 hand and carefully remove the needle from the Pen with your other hand.

See Figure Y.

Throw away (dispose of) the needle. See “How should I dispose of my Pen and needles?” at the end of these instructions.

Put the PenMate cap back on your PenMate after each use to protect the growth hormone from direct light.

See Figure Z.

Important safety information to remember:

- Be careful not to drop your PenMate and Pen or knock them against a hard surface. If this happens you will need to check the growth hormone flow.
- Do not try to put the inner needle cap back on the needle. You may stick yourself with the needle. Be careful when handling used needles to avoid needle stick injuries.
- After each use always remove and throw away (dispose of) the needle from your Pen.
- Do not share your Pen or needles with other people.
- If your PenMate is damaged or lost, you can still use your Pen without your PenMate.
- Always keep your Pen and needles out of reach of others, especially children.

How should I replace an empty Pen?

PenMate is reusable and should not be thrown away (disposed of). Reuse your PenMate by replacing your Pen when it is empty.

When your Pen is empty, twist the Pen counterclockwise until you hear or feel a click.

See Figure AA.

Gently pull the Pen out of PenMate.

See Figure BB.

Before throwing away (disposing of) your empty Pen, make sure the needle has been removed. See “How should I dispose of my Pen and needles?” at the end of these instructions.

Insert the new Pen into your PenMate.

See Figure CC.

Twist the Pen clockwise until you hear or feel a click.

See Figure DD.

The Pen is correctly attached in your PenMate when the display window on the Pen lines up with the insertion button on your PenMate.

How should I store my PenMate and Pen?

- Do not expose your PenMate or Pen to dust, dirt, liquid, or direct light.
- Store your PenMate and Pen in their case. See Figure D at the beginning of these instructions.
- When your Pen is inserted in PenMate, store it as described in the Patient Information leaflet that comes with your Pen.

How should I care for and clean my Pen with PenMate?

- Do not try to refill your Pen. It is prefilled.
- Do not try to repair your PenMate or your Pen.
- Only clean your PenMate or Pen with a mild detergent on a moistened cloth.
- Do not wash, soak, or lubricate your PenMate or Pen. Do not use products containing bleaching agents, such as chlorine, iodine, or alcohol to clean your PenMate or Pen. These products may damage them.
- If there is liquid growth hormone on the outside of your PenMate or Pen, clean it with a mild detergent on a moistened cloth before it dries up.

How should I throw away (dispose of) my Pen and needles?

- Put your used needles and Pens in a FDA-cleared sharps disposal container right away after use. Do not throw away (dispose of) loose needles and Pens in your household trash.
- If you do not have a FDA-cleared sharps disposal container, you may use a household container that is:
  - made of a heavy-duty plastic,
  - can be closed with a tight-fitting, puncture-resistant lid, without sharps being able to come out,
  - upright and stable during use,
  - leak-resistant, and
  - properly labeled to warn of hazardous waste inside the container.
- When your sharps disposal container is almost full, you will need to follow your community guidelines for the right way to dispose of your sharps disposal container. There may be state or local laws about how you should throw away used needles and Pens. For more information about safe sharps disposal, and for specific information about sharps disposal in the state that you live in, go to the FDA’s website at: http://www.fda.gov/safesharpsdisposal.
- Do not dispose of your used sharps disposal container in your household trash unless your community guidelines permit this. Do not recycle your used sharps disposal container.

Need help?

PenMate must only be used according to the instructions provided. The manufacturer cannot be held responsible for any problems with PenMate if these instructions have not been followed.

If you find that your PenMate or case is defective, make sure to have Novo Nordisk replace it. Call the number below to order a new PenMate or case and arrange return of the defective item for inspection.

For help or further information, write to:

Novo Nordisk Inc.

800 Scudders Mill Road

Plainsboro, NJ 08536, USA

Visit norditropin.com or sogroya.com

Or call: 1-888-668-6444

PATENT Information: http://novonordisk-us.com/products/product-patents.html

Novo Nordisk®, PenMate® and NovoFine® are registered trademarks of Novo Nordisk A/S

Norditropin®, Sogroya® and FlexPro® are registered trademarks of Novo Nordisk Health Care AG.

© 2025 Novo Nordisk A/S

Manufactured by:

Novo Nordisk A/S

Novo Allé

DK-2880 Bagsvaerd

Denmark

This Instructions for Use has been approved by the U.S. Food and Drug Administration.

Issued: 01/2025

PRINCIPAL DISPLAY PANEL - NORDITROPIN FLEXPRO 5 MG/1.5 ML

NDC 0169-7704-21

List: 770421

5 mg

Norditropin® FlexPro®

(somatropin) injection

5 mg/1.5 mL Prefilled Pen

For subcutaneous use

Contains 1 x 1.5 mL single-patient-use prefilled pen

Rx only

PRINCIPAL DISPLAY PANEL - NORDITROPIN FLEXPRO 10 MG/1.5 ML

NDC 0169-7705-21

List: 770521

10 mg

Norditropin® FlexPro®

(somatropin) injection

10 mg/1.5 mL Prefilled Pen

Contains 1 x 1.5 mL single-patient-use prefilled pen

Rx only

PRINCIPAL DISPLAY PANEL - NORDITROPIN FLEXPRO 15 MG/1.5 ML

NDC 0169-7708-21

List: 770821

15 mg

Norditropin® FlexPro®

(somatropin) injection

For subcutaneous use

Contains 1 x 1.5 mL single-patient-use prefilled pen

Rx only

PRINCIPAL DISPLAY PANEL - NORDITROPIN FLEXPRO 30 MG/3 ML

NDC 0169-7703-21

List: 770321

30 mg

Norditropin® FlexPro®

(somatropin) injection

30 mg / 3 mLPrefilled Pen

For subcutaneous use

Contains 1 x 3 mL single-patient-use prefilled pen

Rx only